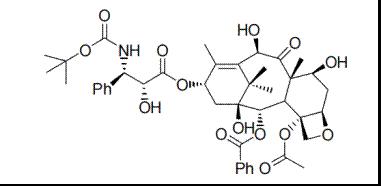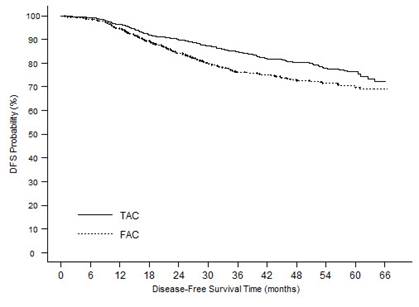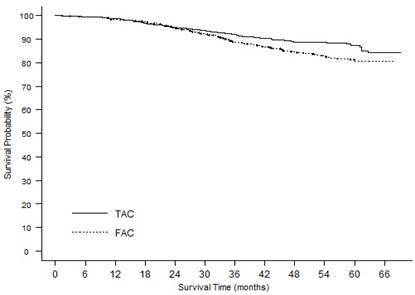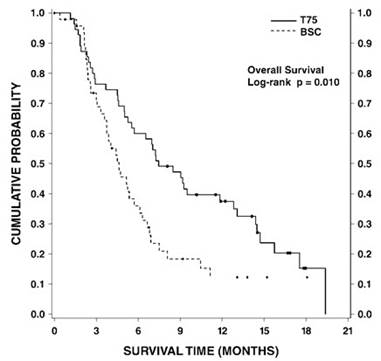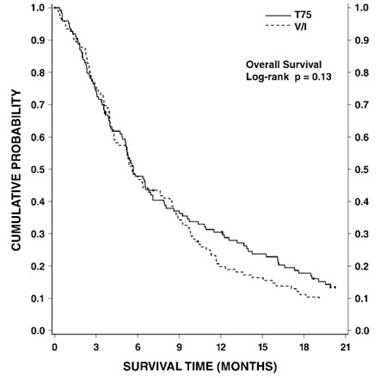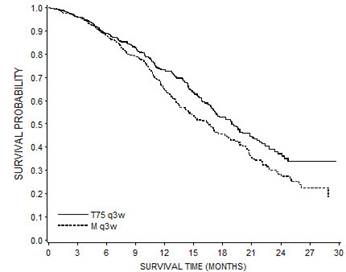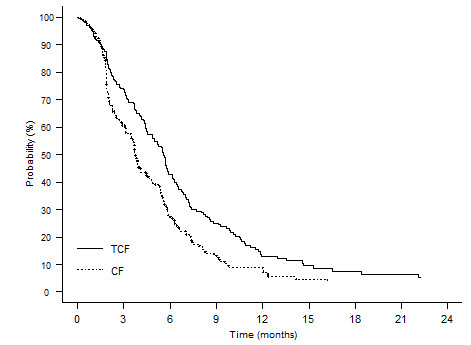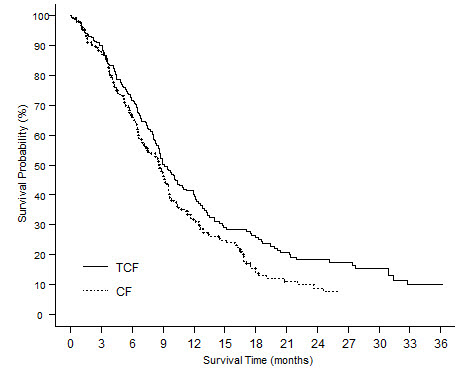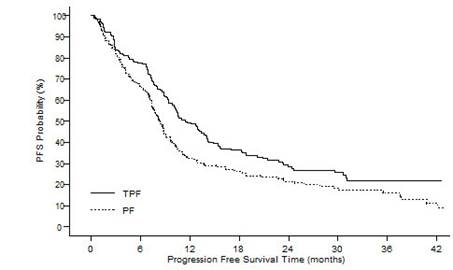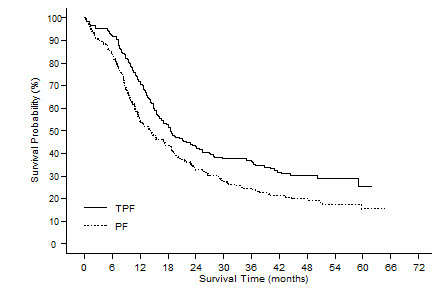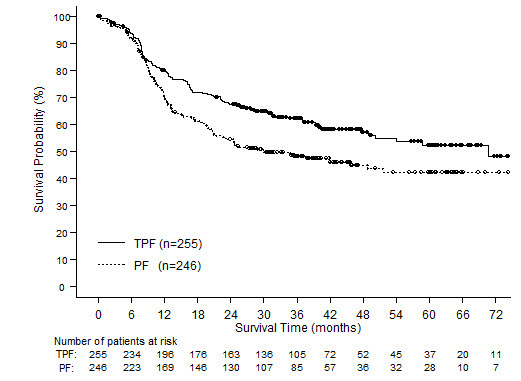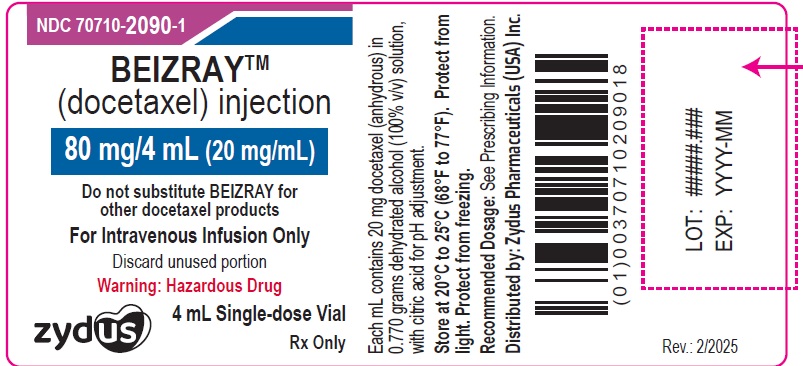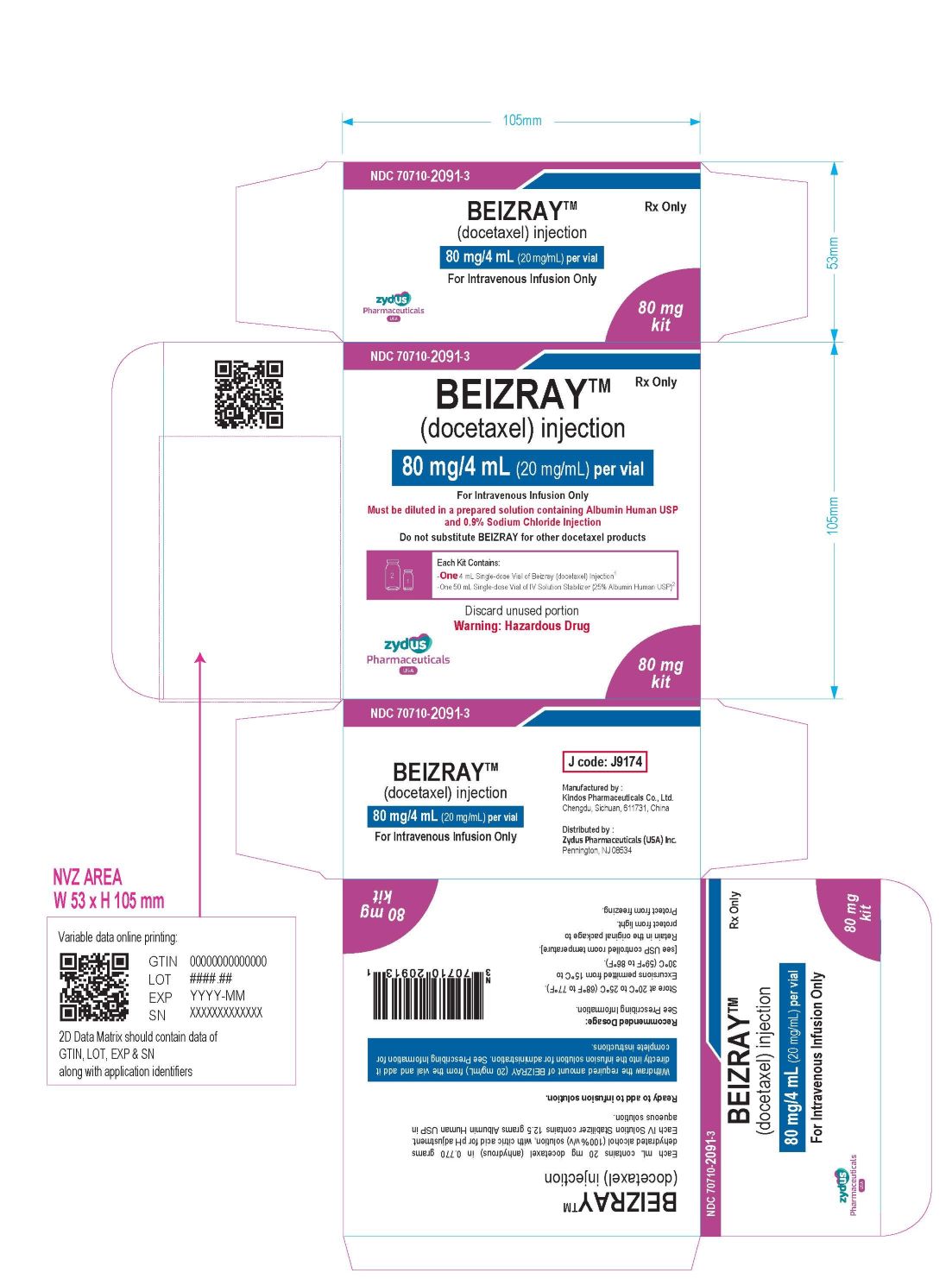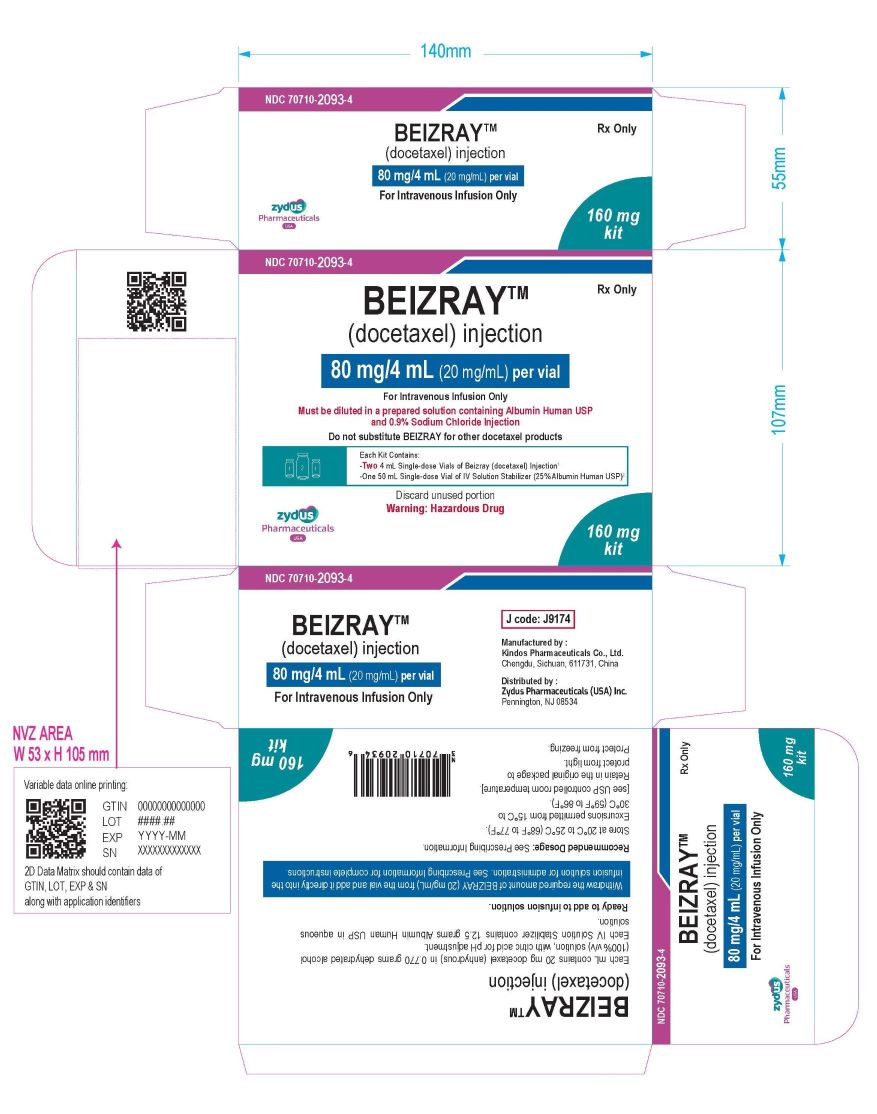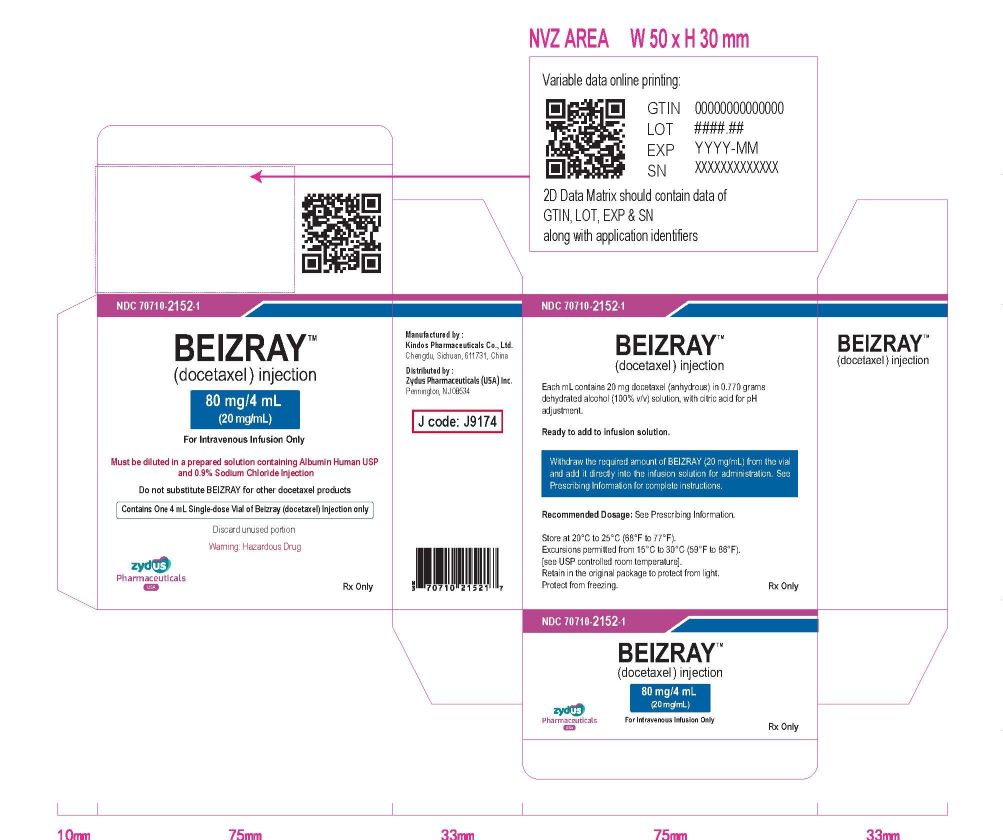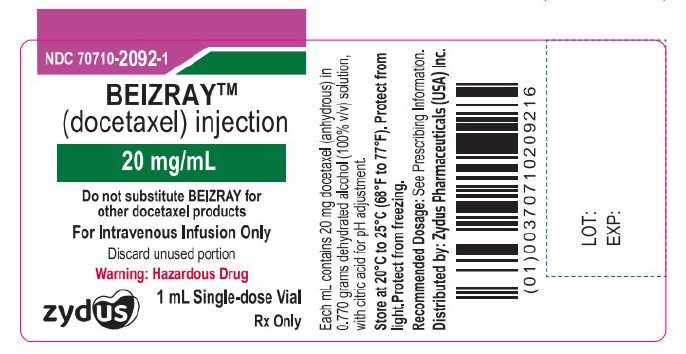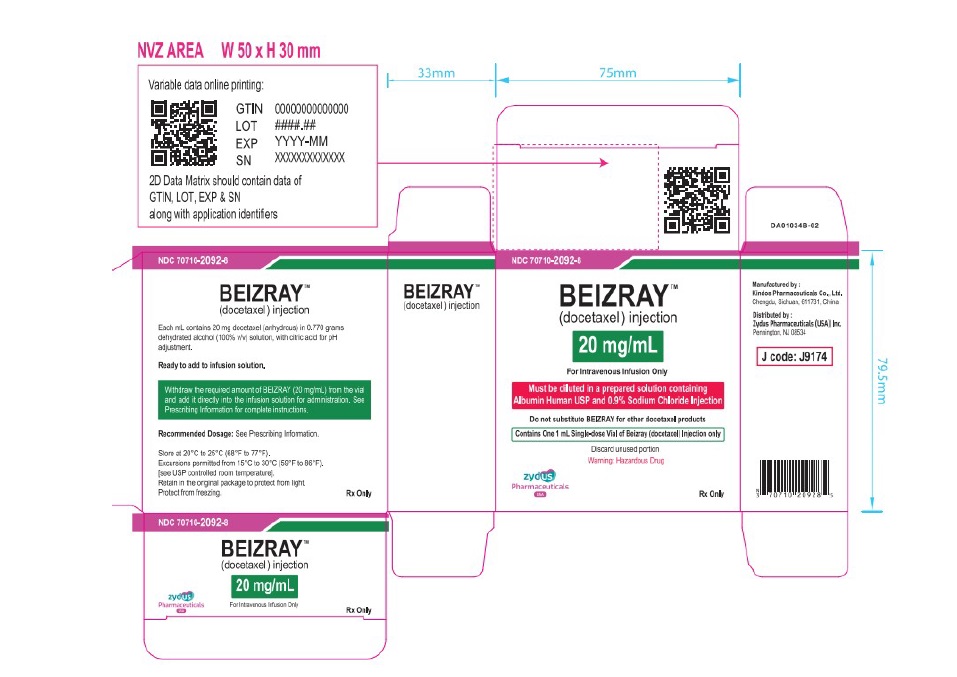 DRUG LABEL: BEIZRAY

NDC: 70710-2091 | Form: KIT | Route: INTRAVENOUS
Manufacturer: Zydus Pharmaceuticals USA Inc.
Category: prescription | Type: HUMAN PRESCRIPTION DRUG LABEL
Date: 20251217

ACTIVE INGREDIENTS: DOCETAXEL ANHYDROUS 20 mg/1 mL; ALBUMIN HUMAN 0.25 g/1 mL
INACTIVE INGREDIENTS: ALCOHOL; CITRIC ACID ACETATE; CAPRYLIC ACID; N-ACETYL-DL-TRYPTOPHAN SODIUM; SODIUM CHLORIDE; SODIUM HYDROXIDE

HIGHLIGHTS OF PRESCRIBING INFORMATION

These highlights do not include all the information needed to use BEIZRAY safely and effectively. See full prescribing information for BEIZRAY.
BEIZRAY (docetaxel) injection, for intravenous use
Initial U.S. Approval: 1996

WARNING: TOXIC DEATHS, HEPATOTOXICITY, NEUTROPENIA, HYPERSENSITIVITY REACTIONS, and FLUID RETENTION

See full prescribing information for complete boxed warning.

- Treatment-related mortality increases with abnormal liverfunction, at higher doses, and in patients with NSCLC and prior platinum-based therapy receiving BEIZRAY at 100 mg/m^2(5.1)
- Avoid use of BEIZRAY if bilirubin > ULN, or if AST and/or ALT >1.5 × ULN concomitant with alkaline phosphatase >2.5 × ULN. LFT elevations increase risk of severe or life-threatening complications. Obtain LFTs before each treatment cycle (5.2)
- Do not administer BEIZRAY to patients with neutrophil counts <1500 cells/mm^3. Obtain frequent blood counts to monitor for neutropenia (4, 5.3)
- Severe hypersensitivity, including fatal anaphylaxis, has been reported in patients who received dexamethasone premedication. Severe reactions require immediate discontinuation of BEIZRAY and administration of appropriate therapy (5.5)
- Contraindicated if history of severe hypersensitivity reactions to docetaxel (4)
- Severe fluid retention may occur despite dexamethasone (5.6)

1 INDICATIONS AND USAGE

BEIZRAY is a microtubule inhibitor indicated for:

- Breast Cancer (BC): single agent for locally advanced or metastatic BC after chemotherapy failure; and with doxorubicin and cyclophosphamide as adjuvant treatment of operable node-positive BC (1.1)
- Non-small Cell Lung Cancer (NSCLC): single agent for locally advanced or metastatic NSCLC after platinum therapy failure; and with cisplatin for unresectable, locally advanced or metastatic untreated NSCLC (1.2)
- Castration-Resistant Prostate Cancer (CRPC): with prednisone in metastatic castration-resistant prostate cancer (1.3)
- Gastric Adenocarcinoma (GC): with cisplatin and fluorouracil for untreated, advanced GC, including the gastroesophageal junction (1.4)
- Squamous Cell Carcinoma of the Head and Neck (SCCHN): with cisplatin and fluorouracil for induction treatment of locally advanced SCCHN (1.5)

2 DOSAGE AND ADMINISTRATION

- Do not substitute BEIZRAY for other docetaxel products. (2.1)

Administer in a facility equipped to manage possible complications (e.g., anaphylaxis). Administer intravenously (IV) over 1 hour every 3 weeks.

- BC locally advanced or metastatic: 60 mg/m^2to 100 mg/m^2single agent (2.2)
- BC adjuvant: 75 mg/m^2administered 1 hour after doxorubicin 50 mg/m^2and cyclophosphamide 500 mg/m^2every 3 weeks for 6 cycles (2.2)
- NSCLC: after platinum therapy failure: 75 mg/m^2single agent (2.3)
- NSCLC: chemotherapy naive: 75 mg/m^2followed by cisplatin 75 mg/m^2(2.3)
- CRPC: 75 mg/m^2with 5 mg prednisone twice a day continuously (2.4)
- GC: 75 mg/m^2followed by cisplatin 75 mg/m^2(both on day 1 only) followed by fluorouracil 750 mg/m^2per day as a 24-hr IV (days 1-5), starting at end of cisplatin infusion (2.5)
- SCCHN: 75 mg/ m^2followed by cisplatin 75 mg/m^2IV (day 1), followed by fluorouracil 750 mg/m^2per day as a 24-hr IV (days 1-5), starting at end of cisplatin infusion; for 4 cycles (2.6)
- SCCHN: 75 mg/m^2followed by cisplatin 100 mg/m^2IV (day 1), followed by fluorouracil 1000 mg/m^2per day as a 24-hr IV (days 1-4); for 3 cycles (2.6)

For all patients:

- Premedicate with oral corticosteroids (2.7)
- Adjust dose as needed (2.8)

3 DOSAGE FORMS AND STRENGTHS

BEIZRAY (docetaxel) injection is supplied as follows:

BEIZRAY 80 mg kit contains:

- One single-dose vial of BEIZRAY: 80 mg/4 mL (3)
- One single-dose vial of IV Solution Stabilizer (50 mL, 25% Albumin Human USP solution) (3)

BEIZRAY 160 mg kit contains:

- Two single-dose vials of BEIZRAY: 80 mg/4 mL each (3)
- One single-dose vial of IV Solution Stabilizer (50 mL, 25% Albumin Human USP solution) (3)

BEIZRAY carton containing one single-dose vial:

- 80 mg/4 mL (3)
- 20 mg/mL (3)

4 CONTRAINDICATIONS

- Hypersensitivity to docetaxel (4)
- Neutrophil counts of <1500 cells/mm ^3(4)

5 WARNINGS AND PRECAUTIONS

- Second primary malignancies: In patients treated with BEIZRAY-containing regimens, monitor for delayed AML, MDS, NHL, and renal cancer. (5.7)
- Cutaneous reactions: Reactions including erythema of the extremities with edema followed by desquamation may occur. Severe cutaneous adverse reactions have been reported. Severe skin toxicity may require dose adjustment or permanent treatment discontinuation. (5.8)
- Neurologic reactions: Reactions including paresthesia, dysesthesia, and pain may occur. Severe neurosensory symptoms require dose adjustment or discontinuation if persistent. (5.9)
- Eye disorders: Cystoid macular edema (CME) has been reported and requires treatment discontinuation. (5.10)
- Asthenia: Severe asthenia may occur and may require treatment discontinuation. (5.11)
- Embryo-fetal toxicity: Can cause fetal harm. Advise patients of the potential risk to a fetus and to use effective contraception. (5.12, 8.1, 8.3)
- Alcohol content: The alcohol content in a dose of BEIZRAY Injection may affect the central nervous system. This may include impairment of a patient's ability to drive or use machines immediately after infusion. (5.13)
- Tumor lysis syndrome: Tumor lysis syndrome has been reported. Patients at risk should be well hydrated and closely monitored during treatment. (5.14)
- BEIZRAY final infusion solution contains albumin derived from human blood, which has a theoretical risk of viral transmission. (5.15)

6 ADVERSE REACTIONS

Most common adverse reactions across all BEIZRAY indications are infections, neutropenia, anemia, febrile neutropenia, hypersensitivity, thrombocytopenia, neuropathy, dysgeusia, dyspnea, constipation, anorexia, nail disorders, fluid retention, asthenia, pain, nausea, diarrhea, vomiting, mucositis, alopecia, skin reactions, and myalgia. (6)

To report SUSPECTED ADVERSE REACTIONS, contact Zydus Pharmaceuticals (USA) Inc. at 1-877-993-8779 or FDA at 1-800-FDA-1088 or www.fda.gov/medwatch.

7 DRUG INTERACTIONS

- Cytochrome P450 3A4 inducers, inhibitors, or substrates: May alter docetaxel metabolism. (7)

8 USE IN SPECIFIC POPULATIONS

- Lactation: Advise women not to breastfeed. (8.2)
- Females and Males of Reproductive Potential: Verify pregnancy status of females prior to initiation of BEIZRAY. (8.3)

FULL PRESCRIBING INFORMATION

WARNING: TOXIC DEATHS, HEPATOTOXICITY, NEUTROPENIA, HYPERSENSITIVITY REACTIONS, and FLUID RETENTION

Treatment-related mortality associated with BEIZRAY is increased in patients with abnormal liver function, in patients receiving higher doses, and in patients with non- small cell lung carcinoma and a history of prior treatment with platinum-based chemotherapy who receive BEIZRAY as a single agent at a dose of 100 mg/m^2 [see Warnings and Precautions (5.1)].

Avoid the use of BEIZRAY in patients with bilirubin > upper limit of normal (ULN), or to patients with AST and/or ALT >1.5 × ULN concomitant with alkaline phosphatase >2.5 × ULN. Patients with elevations of bilirubin or abnormalities of transaminase concurrent with alkaline phosphatase are at increased risk for the development of severe neutropenia, febrile neutropenia, infections, severe thrombocytopenia, severe stomatitis, severe skin toxicity, and toxic death. Patients with isolated elevations of transaminase >1.5 × ULN also had a higher rate of febrile neutropenia. Measure bilirubin, AST or ALT, and alkaline phosphatase prior to each cycle of BEIZRAY [see Warnings and Precautions (5.2)].

Do not administer BEIZRAY to patients with neutrophil counts of <1500 cells/mm^3. Monitor blood counts frequently as neutropenia may be severe and result in infection. [see Warnings and Precautions (5.3)].

Do not administer BEIZRAY to patients who have a history of severe hypersensitivity reactions to docetaxel [see Contraindications (4)]. Severe hypersensitivity reactions have been reported in patients despite dexamethasone premedication. Hypersensitivity reactions require immediate discontinuation of the BEIZRAY infusion and administration of appropriate therapy [see Warnings and Precautions (5.5)].

Severe fluid retention occurred in 6.5% (6/92) of patients despite use of dexamethasone premedication. It was characterized by one or more of the following events: poorly tolerated peripheral edema, generalized edema, pleural effusion requiring urgent drainage, dyspnea at rest, cardiac tamponade, or pronounced abdominal distention (due to ascites) [see Warnings and Precautions (5.6)].

1 INDICATIONS AND USAGE

1.1 Breast Cancer

BEIZRAY is indicated for the treatment of patients with locally advanced or metastatic breast cancer after failure of prior chemotherapy.

BEIZRAY in combination with doxorubicin and cyclophosphamide is indicated for the adjuvant treatment of patients with operable node-positive breast cancer.

1.2 Non-small Cell Lung Cancer

BEIZRAY as a single agent is indicated for the treatment of patients with locally advanced or metastatic non-small cell lung cancer after failure of prior platinum-based chemotherapy.

BEIZRAY in combination with cisplatin is indicated for the treatment of patients with unresectable, locally advanced or metastatic non-small cell lung cancer who have not previously received chemotherapy for this condition.

1.3 Prostate Cancer

BEIZRAY in combination with prednisone is indicated for the treatment of patients with metastatic castration-resistant prostate cancer.

1.4 Gastric Adenocarcinoma

BEIZRAY in combination with cisplatin and fluorouracil is indicated for the treatment of patients with advanced gastric adenocarcinoma, including adenocarcinoma of the gastroesophageal junction, who have not received prior chemotherapy for advanced disease.

1.5 Head and Neck Cancer

BEIZRAY in combination with cisplatin and fluorouracil is indicated for the induction treatment of patients with locally advanced squamous cell carcinoma of the head and neck (SCCHN).

2 DOSAGE AND ADMINISTRATION

2.1 Important Dosage and Administration Instructions

Do not substitute BEIZRAY for or with other docetaxel products because BEIZRAY has different administration instructions from other docetaxel products.

For all indications, toxicities may warrant dosage adjustments [see Dosage and Administration (2.8)].

Administer in a facility equipped to manage possible complications (e.g. anaphylaxis).

See additional premedication recommendations for the indicated populations [see Dosage and Administration (2.7)]

2.2 Recommended Dosage for Breast Cancer

For locally advanced or metastatic breast cancer after failure of prior chemotherapy, the recommended dosage of BEIZRAY is 60 mg/m^2 to 100 mg/m^2 administered intravenously over 1 hour every 3 weeks.

For the adjuvant treatment of operable node-positive breast cancer, the recommended BEIZRAY dosage is 75 mg/m^2 administered 1 hour after doxorubicin 50 mg/m^2 and cyclophosphamide 500 mg/m^2 every 3 weeks for 6 courses. Prophylactic G-CSF may be used to mitigate the risk of hematological toxicities [see Dosage and Administration (2.7)].

2.3 Recommended Dosage for Non-small Cell Lung Cancer

For treatment after failure of prior platinum-based chemotherapy, the recommended dosage of BEIZRAY monotherapy is 75 mg/m^2 administered intravenously over 1 hour every 3 weeks.

In patients previously treated with chemotherapy, a dosage of 100 mg/m^2 is not recommended because this dosage was associated with increased hematologic toxicity, infection, and treatment-related mortality in randomized controlled trials [see Dosage and Administration (2.8), Warnings and Precautions (5), and Clinical Studies (14)].

For chemotherapy-naive patients, the recommended dosage of BEIZRAY is 75 mg/m^2 administered intravenously over 1 hour immediately followed by cisplatin 75 mg/m^2 over 30-60 minutes every 3 weeks [see Dosage and Administration (2.7)].

2.4 Recommended Dosage for Prostate Cancer

For metastatic castration-resistant prostate cancer, the recommended dosage of BEIZRAY is 75 mg/m^2 every 3 weeks as a 1-hour intravenous infusion. Recommend concomitant use of 5 mg of prednisone orally twice daily continuously [see Dosage and Administration (2.7)].

2.5 Recommended Dosage for Gastric Adenocarcinoma

For gastric adenocarcinoma, the recommended dosage of BEIZRAY is 75 mg/m^2 as a 1-hour intravenous infusion, followed by cisplatin 75 mg/m^2, as a 1 to 3 hour intravenous infusion (both on day 1 only), followed by fluorouracil 750 mg/m^2 per day given as a 24-hour continuous intravenous infusion for 5 days, starting at the end of the cisplatin infusion.

Repeat treatment every three weeks. Must receive premedication with antiemetics and appropriate hydration for cisplatin administration [see Dosage and Administration (2.7)].

2.6 Recommended Dosage for Head and Neck Cancer

Must receive premedication with antiemetics, and appropriate hydration (prior to and after cisplatin administration). Prophylaxis for neutropenic infections should be administered. All patients treated on the BEIZRAY containing arms of the TAX323 and TAX324 studies received prophylactic antibiotics.

Induction Chemotherapy Followed by Radiotherapy (TAX323)

For the induction treatment of locally advanced inoperable SCCHN, the recommended dose of BEIZRAY is 75 mg/m^2 as a 1 hour intravenous infusion followed by cisplatin 75 mg/m^2 intravenously over 1 hour, on day one, followed by fluorouracil as a continuous intravenous infusion at 750 mg/m^2 per day for five days. This regimen is administered every 3 weeks for 4 cycles. Following chemotherapy, patients should receive radiotherapy [see Dosage and Administration (2.7)].

Induction Chemotherapy Followed by Chemoradiotherapy (TAX324)

For the induction treatment of patients with locally advanced (unresectable, low surgical cure, or organ preservation) SCCHN, the recommended dose of BEIZRAY is 75 mg/m^2 as a 1 hour intravenous infusion on day 1, followed by cisplatin 100 mg/m^2 administered as a 30-minute to 3 hour infusion, followed by fluorouracil 1000 mg/m^2/day as a continuous infusion from day 1 to day 4. This regimen is administered every 3 weeks for 3 cycles. Following chemotherapy, patients should receive chemoradiotherapy [see Dosage and Administration (2.7)].

2.7 Corticosteroid Premedication Regimen

All patients should be premedicated with oral corticosteroids (see below for prostate cancer) such as dexamethasone 16 mg per day (e.g., 8 mg twice daily) for 3 days starting 1 day prior to BEIZRAY administration in order to reduce the incidence and severity of fluid retention as well as the severity of hypersensitivity reactions [see Boxed Warning, Warnings and Precautions (5.5)].

For metastatic castration-resistant prostate cancer, given the concurrent use of prednisone, the recommended premedication regimen is oral dexamethasone 8 mg at 12 hours, 3 hours, and 1 hour before the BEIZRAY infusion [see Warnings and Precautions (5.5)].

2.8 Dosage Adjustments during Treatment

Breast Cancer

Patients who are dosed initially at 100 mg/m^2 and who experience either febrile neutropenia, neutrophils <500 cells/mm^3 for more than 1 week, or severe or cumulative cutaneous reactions during BEIZRAY therapy should have the dosage adjusted from 100 mg/m^2 to 75 mg/m^2. If the patient continues to experience these reactions, the dosage should either be decreased from 75 mg/m^2 to 55 mg/m^2 or the treatment should be discontinued. Conversely, patients who are dosed initially at 60 mg/m^2 and who do not experience febrile neutropenia, neutrophils <500 cells/mm^3 for more than 1 week, severe or cumulative cutaneous reactions, or severe peripheral neuropathy during BEIZRAY therapy may tolerate higher doses. Patients who develop ≥grade 3 peripheral neuropathy should have BEIZRAY treatment discontinued entirely.

Combination Therapy with BEIZRAY in the Adjuvant Treatment of Breast Cancer

BEIZRAY in combination with doxorubicin and cyclophosphamide should be administered when the neutrophil count is ≥1,500 cells/mm^3. Patients who experience febrile neutropenia should receive G-CSF in all subsequent cycles. Patients who continue to experience this reaction should remain on G-CSF and have their BEIZRAY dose reduced to 60 mg/m^2. Patients who experience grade 3 or 4 stomatitis should have their BEIZRAY dose decreased to 60 mg/m^2. Patients who experience severe or cumulative cutaneous reactions or moderate neurosensory signs and/or symptoms during BEIZRAY therapy should have their dosage of BEIZRAY reduced from 75 mg/m^2 to 60 mg/m^2. If the patient continues to experience these reactions at 60 mg/m^2, treatment should be discontinued.

Non-small Cell Lung Cancer

Monotherapy with BEIZRAY for NSCLC treatment after failure of prior platinum-based chemotherapy

Patients who are dosed initially at 75 mg/m^2 and who experience either febrile neutropenia, neutrophils <500 cells/mm^3 for more than one week, severe or cumulative cutaneous reactions, or other grade 3/4 non-hematological toxicities during BEIZRAY treatment should have treatment withheld until resolution of the toxicity and then resumed at 55 mg/m^2. Patients who develop ≥grade 3 peripheral neuropathy should have BEIZRAY treatment discontinued entirely.

Combination therapy with BEIZRAY for chemotherapy-naive NSCLC

For patients who are dosed initially at BEIZRAY 75 mg/m^2 in combination with cisplatin, and whose nadir of platelet count during the previous course of therapy is <25,000 cells/mm^3, in patients who experience febrile neutropenia, and in patients with serious non-hematologic toxicities, the BEIZRAY dosage in subsequent cycles should be reduced to 65 mg/m^2. In patients who require a further dose reduction, a dose of 50 mg/m^2 is recommended. For cisplatin dosage adjustments, see manufacturers' prescribing information.

Prostate Cancer

Combination therapy with BEIZRAY for metastatic castration-resistant prostate cancer

BEIZRAY should be administered when the neutrophil count is ≥1,500 cells/mm^3. Patients who experience either febrile neutropenia, neutrophils <500 cells/mm^3 for more than one week, severe or cumulative cutaneous reactions or moderate neurosensory signs and/or symptoms during BEIZRAY therapy should have the dosage of BEIZRAY reduced from 75 mg/m^2 to 60 mg/m^2. If the patient continues to experience these reactions at 60 mg/m^2, the treatment should be discontinued.

Gastric or Head and Neck Cancer

BEIZRAY in combination with cisplatin and fluorouracil in gastric cancer or head and neck cancer

Patients treated with BEIZRAY in combination with cisplatin and fluorouracil must receive antiemetics and appropriate hydration according to current institutional guidelines. In both studies, G-CSF was recommended during the second and/or subsequent cycles in case of febrile neutropenia, or documented infection with neutropenia, or neutropenia lasting more than 7 days.

If an episode of febrile neutropenia, prolonged neutropenia or neutropenic infection occurs despite G-CSF use, the BEIZRAY dose should be reduced from 75 mg/m^2 to 60 mg/m^2. If subsequent episodes of complicated neutropenia occur the BEIZRAY dose should be reduced from 60 mg/m^2 to 45 mg/m^2. In case of grade 4 thrombocytopenia the BEIZRAY dose should be reduced from 75 mg/m^2 to 60 mg/m^2. Do not retreat patients with subsequent cycles of BEIZRAY until neutrophils recover to a level >1,500 cells/mm^3 [see Contraindications (4)]. Avoid retreating patients until platelets recover to a level >100,000 cells/mm^3. Discontinue treatment if these toxicities persist [see Warnings and Precautions (5.3)].

Recommended dose modifications for toxicities in patients treated with BEIZRAY in combination with cisplatin and fluorouracil are shown in Table 1.

Table 1: Recommended Dose Modifications for Toxicities in Patients Treated with BEIZRAY in Combination with Cisplatin and Fluorouracil
Toxicity | Dosage adjustment
Diarrhea grade 3 | First episode: reduce fluorouracil dose by 20%. Second episode: then reduce BEIZRAY dose by 20%.
Diarrhea grade 4 | First episode: reduce BEIZRAY and fluorouracil doses by 20%. Second episode: discontinue treatment.
Stomatitis/mucositis grade 3 | First episode: reduce fluorouracil dose by 20%. Second episode: stop fluorouracil only, at all subsequent cycles. Third episode: reduce BEIZRAY dose by 20%.
Stomatitis/mucositis grade 4 | First episode: stop fluorouracil only, at all subsequent cycles. Second episode: reduce BEIZRAY dose by 20%.

Liver dysfunction: In case of AST/ALT >2.5 to ≤5 × ULN and AP ≤2.5 × ULN, or AST/ALT >1.5

to ≤5 × ULN and AP >2.5 to ≤5 × ULN, BEIZRAY should be reduced by 20%.

In case of AST/ALT >5 × ULN and/or AP >5 × ULN BEIZRAY should be stopped.

The dose modifications for cisplatin and fluorouracil in the gastric cancer study are provided below.

Cisplatin dose modifications and delays

Peripheral neuropathy: A neurological examination should be performed before entry into the study, and then at least every 2 cycles and at the end of treatment. In the case of neurological signs or symptoms, more frequent examinations should be performed and the following dose modifications can be made according to NCI-CTCAE grade:

• Grade 2: Reduce cisplatin dose by 20%.

• Grade 3: Discontinue treatment.

Ototoxicity: In the case of grade 3 toxicity, discontinue treatment.

Nephrotoxicity: In the event of a rise in serum creatinine ≥grade 2 (>1.5 × normal value) despite adequate rehydration, CrCl should be determined before each subsequent cycle and the following dose reductions should be considered (see Table 2).

For other cisplatin dosage adjustments, also refer to the manufacturers' prescribing information.

Table 2: Dose Reductions for Evaluation of Creatinine Clearance
Creatinine clearance result before next cycle | Cisplatin dose next cycle
CrCl ≥60 mL/min | Full dose of cisplatin was given. CrCl was to be repeated before each treatment cycle.
CrCl between 40 and 59 mL/min | Dose of cisplatin was reduced by 50% at subsequent cycle. If CrCl was >60 mL/min at end of cycle, full cisplatin dose was reinstituted at the next cycle. If no recovery was observed, then cisplatin was omitted from the next treatment cycle.
CrCl <40 mL/min | Dose of cisplatin was omitted in that treatment cycle only. If CrCl was still <40 mL/min at the end of cycle, cisplatin was discontinued. If CrCl was >40 and <60 mL/min at end of cycle, a 50% cisplatin dose was given at the next cycle. If CrCl was >60 mL/min at end of cycle, full cisplatin dose was given at next cycle.
CrCl = Creatinine clearance

Fluorouracil dose modifications and treatment delays

For diarrhea and stomatitis, see Table 1.

In the event of grade 2 or greater plantar-palmar toxicity, fluorouracil should be stopped until recovery. The fluorouracil dosage should be reduced by 20%.

For other greater than grade 3 toxicities, except alopecia and anemia, chemotherapy should be delayed (for a maximum of 2 weeks from the planned date of infusion) until resolution to grade ≤1 and then recommenced, if medically appropriate.

For other fluorouracil dosage adjustments, also refer to the manufacturers' prescribing information.

Combination Therapy with Strong CYP3A4 Inhibitors

Avoid using concomitant strong CYP3A4 inhibitors (e.g., ketoconazole, itraconazole, clarithromycin, atazanavir, indinavir, nefazodone, nelfinavir, ritonavir, saquinavir, telithromycin and voriconazole). There are no clinical data with a dose adjustment in patients receiving strong CYP3A4 inhibitors. Based on extrapolation from a pharmacokinetic study with ketoconazole in 7 patients, consider a 50% docetaxel dose reduction if patients require coadministration of a strong CYP3A4 inhibitor [see Drug Interactions (7), Clinical Pharmacology (12.3)].

2.9 Administration Precautions

BEIZRAY is a hazardous anticancer drug and, as with other potentially toxic compounds, caution should be exercised when handling and preparing BEIZRAY solutions. The use of gloves is recommended [see How Supplied/Storage and Handling (16.3)].

If BEIZRAY or final infusion solution should come into contact with the skin, immediately and thoroughly wash with soap and water. If BEIZRAY or final infusion solution should come into contact with mucosa, immediately and thoroughly wash with water.

The final BEIZRAY infusion solution should be stored in bottles (glass, polypropylene) or plastic bags (polypropylene, polyolefin).

Please follow the preparation instructions provided below.

2.10 Preparation and Administration

BEIZRAY is available in two packaging configurations:

- Co-packaged kit containing BEIZRAY vial(s) and IV Solution Stabilizer (25% Albumin Human USP)
- Carton containing one BEIZRAY vial only

Preparation

Read this entire section carefully before mixing and diluting.

- Inject 25% Albumin Human USP (IV Solution Stabilizer) directly into the 0.9% Sodium Chloride Injection bag. Do not use 25% Albumin Human USP (IV Solution Stabilizer) to dilute BEIZRAY.
- To prevent precipitation, BEIZRAY needs to be diluted with a prepared infusion bag containing Albumin Human USP and 0.9% Sodium Chloride Injection to ensure a final concentration between 0.14 mg/mL and 0.31 mg/mL.

Follow the preparation instructions provided below.

Step 1 – Calculate the required amount of BEIZRAY

Calculate the required amount of BEIZRAY using the following formula:

Required amount of BEIZRAY (mL) = prescribed BEIZRAY dose (mg/m^2) × body surface area (m^2) ÷ 20 (mg/mL)

Step 2 – Determine the required amount of 0.9% Sodium Chloride Injection

Based on the calculated amount of BEIZRAY from Step 1, determine the required amount of 0.9% Sodium Chloride Injection in Table 3.

Table 3: The amount required for 0.9% Sodium Chloride Injection based on calculated amount of BEIZRAY in mL
Calculated amount of BEIZRAY | Size of 0.9% Sodium Chloride Injection Infusion Bag
BEIZRAY ≤ 8.8 mL | 500 mL
BEIZRAY > 8.8 mL | 1,000 mL

Step 3 – Calculate the required amount of 25% Albumin Human USP (IV Solution Stabilizer)

Calculate the required amount of 25% Albumin Human USP (IV Solution Stabilizer) using the following formula:

Required amount of 25% Albumin Human USP (IV Solution Stabilizer) (mL) = Required amount of BEIZRAY (mL) × 6

Step 4 – Add 25% Albumin Human USP (IV Solution Stabilizer) to the infusion bag

1. Withdraw the calculated amount of 25% Albumin Human USP (IV Solution Stabilizer) from the vial and inject into a 0.9% Sodium Chloride Injection bag.
2. Thoroughly mix the diluted solution by gently inverting the bag for at least 5 times. Do not shake. This solution should be used immediately after preparation.

Step 5 – Add BEIZRAY to the final infusion solution

1. Aseptically withdraw the calculated amount of BEIZRAY with a calibrated syringe and inject via a single injection into the infusion bag containing the initial diluted solution with 25% Albumin Human USP (IV Solution Stabilizer) to produce a final concentration between 0.14 mg/mL and 0.31 mg/mL.
2. After injection, remove the syringe and immediately thoroughly mix the final infusion solution by gently inverting the bag for at least 10 times. Do not shake.

Discard any unused portion of BEIZRAY vial(s) and 25% Albumin Human USP (IV Solution Stabilizer) vial(s).

Administration

Prior to administration, visually inspect BEIZRAY final infusion solution for particulate matter or discoloration whenever the solution and container permit. Discard the diluted BEIZRAY infusion solution if the solution is not clear, discolored or appears to have precipitation, it should be discarded.

BEIZRAY infusion solution is supersaturated, therefore may crystallize over time. If crystals appear, the solution must be discarded.

The BEIZRAY infusion solution should be administered intravenously as a 1-hour infusion under ambient room temperature (below 25℃) and lighting conditions.

2.11 Stability

BEIZRAY final infusion solution should be used immediately. However, if stored between 2°C and 8°C (36°F and 46°F), the final infusion solution is stable for 24 hours. If stored at 25°C (77°F), the final infusion solution is stable for 4 hours. BEIZRAY final infusion solution (in 0.9% Sodium Chloride Injection) should be used within 4 hours (including the 1 hour intravenous administration).

3 DOSAGE FORMS AND STRENGTHS

BEIZRAY (docetaxel) injection is a clear, colorless liquid supplied as follows:

BEIZRAY 80 mg kit consisting of the following:

- One single-dose vial of BEIZRAY: 80 mg/4 mL
- One single-dose vial of IV Solution Stabilizer: 50 mL of 25% Albumin Human USP solution for infusion; a clear and slightly viscous solution

BEIZRAY 160 mg kit consisting of the following:

- Two single-dose vials of BEIZRAY: 80 mg/4 mL each
- One single-dose vial of IV Solution Stabilizer: 50 mL of 25% Albumin Human USP solution for infusion; a clear and slightly viscous solution

BEIZRAY carton containing one single-dose vial:

- 80 mg/4 mL
- 20 mg/mL

4 CONTRAINDICATIONS

BEIZRAY is contraindicated in patients with:

- neutrophil counts of <1500 cells/mm^3 [see Warnings and Precautions (5.3)].
- a history of severe hypersensitivity reactions to docetaxel. Severe reactions, including anaphylaxis, have occurred [see Warnings and Precautions (5.5)].

5 WARNINGS AND PRECAUTIONS

5.1 Toxic Deaths

Breast Cancer

BEIZRAY administered at 100 mg/m^2 was associated with deaths considered possibly or probably related to treatment in 2.0% (19/965) of metastatic breast cancer patients, both previously treated and untreated, with normal baseline liver function and in 11.5% (7/61) of patients with various tumor types who had abnormal baseline liver function (AST and/or ALT >1.5 times ULN together with AP >2.5 times ULN). Among patients dosed at 60 mg/m^2, mortality related to treatment occurred in 0.6% (3/481) of patients with normal liver function, and in 3 of 7 patients with abnormal liver function. Approximately half of these deaths occurred during the first cycle. Sepsis accounted for the majority of the deaths.

Non-small Cell Lung Cancer

BEIZRAY administered at a dose of 100 mg/m^2 in patients with locally advanced or metastatic non-small cell lung cancer who had a history of prior platinum-based chemotherapy was associated with increased treatment-related mortality (14% and 5% in two randomized, controlled studies). There were 2.8% treatment-related deaths among the 176 patients treated at the 75 mg/m^2 dose in the randomized trials. Among patients who experienced treatment-related mortality at the 75 mg/m^2 dose level, 3 of 5 patients had an ECOG PS of 2 at study entry [see Dosage and Administration (2.2), Clinical Studies (14)].

5.2 Hepatic Impairment

Patients with elevations of bilirubin or abnormalities of transaminase concurrent with alkaline phosphatase are at increased risk for the development of severe neutropenia, febrile neutropenia, infections, severe thrombocytopenia, severe stomatitis, severe skin toxicity, and toxic death.

Avoid BEIZRAY in patients with bilirubin > upper limit of normal (ULN), or to patients with AST and/or ALT >1.5 × ULN concomitant with alkaline phosphatase >2.5 × ULN [see Warnings and Precautions (5.1)].

For patients with isolated elevations of transaminase >1.5 × ULN, consider BEIZRAY dose modifications [see Dosage and Administration (2.7)].

Measure bilirubin, AST or ALT, and alkaline phosphatase prior to each cycle of BEIZRAY therapy.

5.3 Hematologic Effects

Perform frequent peripheral blood cell counts on all patients receiving BEIZRAY. Do not retreat patients with subsequent cycles of BEIZRAY until neutrophils recover to a level >1500 cells/mm^3 [see Contraindications (4)]. Avoid retreating patients until platelets recover to a level >100,000 cells/mm^3.

A 25% reduction in the dose of BEIZRAY is recommended during subsequent cycles following severe neutropenia (<500 cells/mm^3) lasting 7 days or more, febrile neutropenia, or a grade 4 infection in a BEIZRAY cycle [see Dosage and Administration (2.7)].

Neutropenia (<2000 neutrophils/mm^3) occurs in virtually all patients given 60 mg/m^2 to 100 mg/m^2 of BEIZRAY and grade 4 neutropenia (<500 cells/mm^3) occurs in 85% of patients given 100 mg/m^2 and 75% of patients given 60 mg/m^2. Frequent monitoring of blood counts is, therefore, essential so that dose can be adjusted. BEIZRAY should not be administered to patients with neutrophils <1500 cells/mm^3.

Febrile neutropenia occurred in about 12% of patients given 100 mg/m^2 but was very uncommon in patients given 60 mg/m^2. Hematologic responses, febrile reactions and infections, and rates of septic death for different regimens are dose related [see Adverse Reactions (6.1), Clinical Studies (14)].

Three breast cancer patients with severe liver impairment (bilirubin >1.7 times ULN) developed fatal gastrointestinal bleeding associated with severe drug-induced thrombocytopenia. In gastric cancer patients treated with docetaxel in combination with cisplatin and fluorouracil (TCF), febrile neutropenia and/or neutropenic infection occurred in 12% of patients receiving G-CSF compared to 28% who did not. Patients receiving TCF should be closely monitored during the first and subsequent cycles for febrile neutropenia and neutropenic infection [see Dosage and Administration (2.7), Adverse Reactions (6)].

5.4 Enterocolitis and Neutropenic Colitis

Enterocolitis and neutropenic colitis (typhlitis) have occurred in patients treated with BEIZRAY alone and in combination with other chemotherapeutic agents, despite the coadministration of G-CSF. Caution is recommended for patients with neutropenia, particularly at risk for developing gastrointestinal complications. Enterocolitis and neutropenic enterocolitis may develop at any time, and could lead to death as early as the first day of symptom onset. Monitor patients closely from onset of any symptoms of gastrointestinal toxicity. Inform patients to contact their healthcare provider with new, or worsening symptoms of gastrointestinal toxicity [see Dosage and Administration (2), Warnings and Precautions (5.3), Adverse Reactions (6.2)].

5.5 Hypersensitivity Reactions

Monitor patients closely for hypersensitivity reactions, especially during the first and second infusions. Severe hypersensitivity reactions characterized by generalized rash/erythema, hypotension and/or bronchospasm, or fatal anaphylaxis, have been reported in patients premedicated with 3 days of corticosteroids. Severe hypersensitivity reactions require immediate discontinuation of the BEIZRAY infusion and aggressive therapy. Do not rechallenge patients with a history of severe hypersensitivity reactions with BEIZRAY [see Contraindications (4)].

Patients who have previously experienced a hypersensitivity reaction to paclitaxel may develop a hypersensitivity reaction to docetaxel that may include severe or fatal reactions such as anaphylaxis. Monitor patients with a previous history of hypersensitivity to paclitaxel closely during initiation of BEIZRAY therapy. Hypersensitivity reactions may occur within a few minutes following initiation of a BEIZRAY infusion. If minor reactions such as flushing or localized skin reactions occur, interruption of therapy is not required. All patients should be premedicated with an oral corticosteroid prior to the initiation of the infusion of BEIZRAY [see Dosage and Administration (2.6)].

5.6 Fluid Retention

Severe fluid retention has been reported following BEIZRAY therapy. Patients should be premedicated with oral corticosteroids prior to each BEIZRAY administration to reduce the incidence and severity of fluid retention [see Dosage and Administration (2.6)]. Patients with pre-existing effusions should be closely monitored from the first dose for the possible exacerbation of the effusions.

When fluid retention occurs, peripheral edema usually starts in the lower extremities and may become generalized with a median weight gain of 2 kg.

Among 92 breast cancer patients premedicated with 3-day corticosteroids, moderate fluid retention occurred in 27.2% and severe fluid retention in 6.5%. The median cumulative dose to onset of moderate or severe fluid retention was 819 mg/m^2. Nine of 92 patients (9.8%) of patients discontinued treatment due to fluid retention: 4 patients discontinued with severe fluid retention; the remaining 5 had mild or moderate fluid retention. The median cumulative dose to treatment discontinuation due to fluid retention was 1021 mg/m^2. Fluid retention was completely, but sometimes slowly, reversible with a median of 16 weeks from the last infusion of BEIZRAY to resolution (range: 0 to 42+ weeks). Patients developing peripheral edema may be treated with standard measures, e.g., salt restriction, oral diuretic(s).

5.7 Second Primary Malignancies

Second primary malignancies, notably acute myeloid leukemia (AML), myelodysplastic syndrome (MDS), non-Hodgkin's lymphoma (NHL), and renal cancer, have been reported in patients treated with docetaxel-containing regimens. These adverse reactions may occur several months or years after docetaxel-containing therapy.

Treatment-related AML or MDS has occurred in patients given anthracyclines and/or cyclophosphamide, including use in adjuvant therapy for breast cancer. In the adjuvant breast cancer trial (TAX316) AML occurred in 3 of 744 patients who received docetaxel, doxorubicin and cyclophosphamide (TAC) and in 1 of 736 patients who received fluorouracil, doxorubicin, and cyclophosphamide [see Clinical Studies (14.2)]. In TAC-treated patients, the risk of delayed myelodysplasia or myeloid leukemia requires hematological follow-up. Monitor patients for second primary malignancies [see Adverse Reactions (6.1)].

5.8 Cutaneous Reactions

Localized erythema of the extremities with edema followed by desquamation has been observed. In case of severe skin toxicity, an adjustment in dosage is recommended [see Dosage and Administration (2.7)]. The discontinuation rate due to skin toxicity was 1.6% (15/965) for metastatic breast cancer patients. Among 92 breast cancer patients premedicated with 3-day corticosteroids, there were no cases of severe skin toxicity reported and no patient discontinued docetaxel due to skin toxicity.

Severe cutaneous adverse reactions (SCARs) such as Stevens-Johnson syndrome (SJS), toxic epidermal necrolysis (TEN), and acute generalized exanthematous pustulosis (AGEP) have been reported in association with docetaxel treatment. Patients should be informed about the signs and symptoms of serious skin manifestations and monitored closely. Permanent treatment discontinuation should be considered in patients who experience SCARs.

5.9 Neurologic Reactions

Severe neurosensory symptoms (e.g. paresthesia, dysesthesia, pain) were observed in 5.5% (53/965) of metastatic breast cancer patients, and resulted in treatment discontinuation in 6.1%. When these symptoms occur, dosage must be adjusted. If symptoms persist, treatment should be discontinued [see Dosage and Administration (2.7)]. Patients who experienced neurotoxicity in clinical trials and for whom follow-up information on the complete resolution of the event was available had spontaneous reversal of symptoms with a median of 9 weeks from onset (range: 0 to 106 weeks). Severe peripheral motor neuropathy mainly manifested as distal extremity weakness occurred in 4.4% (42/965).

5.10 Eye Disorders

Cystoid macular edema (CME) has been reported in patients treated with docetaxel. Patients with impaired vision should undergo a prompt and comprehensive ophthalmologic examination. If CME is diagnosed, BEIZRAY treatment should be discontinued and appropriate treatment initiated. Alternative non-taxane cancer treatment should be considered.

5.11 Asthenia

Severe asthenia has been reported in 14.9% (144/965) of metastatic breast cancer patients but has led to treatment discontinuation in only 1.8%. Symptoms of fatigue and weakness may last a few days up to several weeks and may be associated with deterioration of performance status in patients with progressive disease.

5.12 Embryo-Fetal Toxicity

Based on findings from animal reproduction studies and its mechanism of action, BEIZRAY can cause fetal harm when administered to a pregnant woman [see Clinical Pharmacology (12.1)]. Available data from case reports in the literature and pharmacovigilance with docetaxel use in pregnant women are not sufficient to inform the drug-associated risk of major birth defects, miscarriage or adverse maternal or fetal outcomes. In animal reproduction studies, administration of docetaxel to pregnant rats and rabbits during the period of organogenesis caused embryo-fetal toxicities, including intrauterine mortality, at doses as low as 0.02 and 0.003 times the recommended human dose based on body surface area, respectively.

Advise pregnant women and females of reproductive potential of the potential risk to a fetus. Verify pregnancy status in females of reproductive potential prior to initiating BEIZRAY. Advise females of reproductive potential to use effective contraception during treatment and for 2 months after the last dose of BEIZRAY. Advise male patients with female partners of reproductive potential to use effective contraception during treatment and for 4 months after the last dose of BEIZRAY [see Use in Specific Populations (8.1, 8.3)].

5.13 Alcohol Content

Cases of intoxication have been reported with some formulations of docetaxel due to the alcohol content. The alcohol content in a dose of BEIZRAY Injection may affect the central nervous system and should be taken into account for patients in whom alcohol intake should be avoided or minimized. Consideration should be given to the alcohol content in BEIZRAY Injection on the ability to drive or use machines immediately after the infusion. Each administration of BEIZRAY Injection at 100 mg/m^2 delivers 4.0 g/m^2 of ethanol. For a patient with a BSA of 2.0 m^2, this would deliver 8.0 grams of ethanol [see Description (11)]. Other docetaxel products may have a different amount of alcohol.

5.14 Tumor Lysis Syndrome

Tumor lysis syndrome has been reported with docetaxel [see Adverse Reactions (6.2)]. Patients at risk of tumor lysis syndrome (e.g., with renal impairment, hyperuricemia, bulky tumor) should be closely monitored prior to initiating BEIZRAY and periodically during treatment. Correction of dehydration and treatment of high uric acid levels are recommended prior to initiation of treatment.

5.15 Transmissible Infectious Agents

BEIZRAY final infusion solution contains Albumin Human USP, a derivative of human blood. Based on effective donor screening and product manufacturing processes, it carries a remote risk for transmission of viral diseases. A theoretical risk for transmission of Creutzfeldt-Jakob Disease (CJD) also is considered extremely remote. No cases of transmission of viral diseases or CJD have ever been identified for albumin.

6 ADVERSE REACTIONS

The most serious adverse reactions from BEIZRAY are:

- Toxic Deaths [see Boxed Warning, Warnings and Precautions (5.1)]
- Hepatic Impairment [see Boxed Warning, Warnings and Precautions (5.2)]
- Hematologic Effects [see Boxed Warning, Warnings and Precautions (5.3)]
- Enterocolitis and Neutropenic Colitis [see Warnings and Precautions (5.4)]
- Hypersensitivity Reactions [see Boxed Warning, Warnings and Precautions (5.5)]
- Fluid Retention [see Boxed Warning, Warnings and Precautions (5.6)]
- Second Primary Malignancies [see Warnings and Precautions (5.7)]
- Cutaneous Reactions [see Warnings and Precautions (5.8)]
- Neurologic Reactions [see Warnings and Precautions (5.9)]
- Eye Disorders [see Warnings and Precautions (5.10)]
- Asthenia [see Warnings and Precautions (5.11)]
- Alcohol Content [see Warnings and Precautions (5.13)]
- Tumor Lysis Syndrome [see Warnings and Precautions (5.14)]

The most common adverse reactions across all docetaxel indications are infections, neutropenia, anemia, febrile neutropenia, hypersensitivity, thrombocytopenia, neuropathy, dysgeusia, dyspnea, constipation, anorexia, nail disorders, fluid retention, asthenia, pain, nausea, diarrhea, vomiting, mucositis, alopecia, skin reactions, and myalgia. Incidence varies depending on the indication.

Adverse reactions are described according to indication. Because clinical trials are conducted under widely varying conditions, adverse reaction rates observed in the clinical trials of a drug cannot be directly compared to rates in the clinical trials of another drug and may not reflect the rates observed in practice.

Responding patients may not experience an improvement in performance status on therapy and may experience worsening. The relationship between changes in performance status, response to therapy, and treatment-related side effects has not been established.

6.1 Clinical Trials Experience

Breast Cancer

Monotherapy with docetaxel for locally advanced or metastatic breast cancer after failure of prior chemotherapy

Docetaxel 100 mg/m^2: Adverse drug reactions occurring in at least 5% of patients are compared for three populations who received docetaxel administered at 100 mg/m^2 as a 1-hour infusion every 3 weeks: 2045 patients with various tumor types and normal baseline liver function tests; the subset of 965 patients with locally advanced or metastatic breast cancer, both previously treated and untreated with chemotherapy, who had normal baseline liver function tests; and an additional 61 patients with various tumor types who had abnormal liver function tests at baseline. These reactions were described using COSTART terms and were considered possibly or probably related to docetaxel. At least 95% of these patients did not receive hematopoietic support. The safety profile is generally similar in patients receiving docetaxel for the treatment of breast cancer and in patients with other tumor types. (See Table 4.)

Table 4: Summary of Adverse Reactions in Patients Receiving Docetaxel at 100 mg/m^2
Adverse Reaction | All Tumor Types Normal LFTs* n=2045 % | All Tumor Types Elevated LFTs** n=61 % | Breast Cancer Normal LFTs* n=965 %
Hematologic
Neutropenia
<2000 cells/mm^3 | 96 | 96 | 99
<500 cells/mm^3 | 75 | 88 | 86
Leukopenia
<4000 cells/mm^3 | 96 | 98 | 99
<1000 cells/mm^3 | 32 | 47 | 44
Thrombocytopenia
<100,000 cells/mm^3 | 8 | 25 | 9
Anemia
<11 g/dL | 90 | 92 | 94
<8 g/dL | 9 | 31 | 8
Febrile Neutropenia*** | 11 | 26 | 12
Septic Death | 2 | 5 | 1
Non-Septic Death | 1 | 7 | 1
Infections
Any | 22 | 33 | 22
Severe | 6 | 16 | 6
Fever in Absence of Infection
Any | 31 | 41 | 35
Severe | 2 | 8 | 2
Hypersensitivity Reactions
Regardless of Premedication
Any | 21 | 20 | 18
Severe | 4 | 10 | 3
With 3-day Premedication | n=92 | n=3 | n=92
Any | 15 | 33 | 15
Severe | 2 | 0 | 2
Fluid Retention
Regardless of Premedication
Any | 47 | 39 | 60
Severe | 7 | 8 | 9
With 3-day Premedication | n=92 | n=3 | n=92
Any | 64 | 67 | 64
Severe | 7 | 33 | 7
Neurosensory
Any | 49 | 34 | 58
Severe | 4 | 0 | 6
Cutaneous
Any | 48 | 54 | 47
Severe | 5 | 10 | 5
Nail Changes
Any | 31 | 23 | 41
Severe | 3 | 5 | 4
Gastrointestinal
Nausea | 39 | 38 | 42
Vomiting | 22 | 23 | 23
Diarrhea | 39 | 33 | 43
Severe | 5 | 5 | 6
Stomatitis
Any | 42 | 49 | 52
Severe | 6 | 13 | 7
Alopecia | 76 | 62 | 74
Asthenia
Any | 62 | 53 | 66
Severe | 13 | 25 | 15
Myalgia
Any | 19 | 16 | 21
Severe | 2 | 2 | 2
Arthralgia | 9 | 7 | 8
Infusion Site Reactions | 4 | 3 | 4
*Normal Baseline LFTs: Transaminases ≤1.5 times ULN or alkaline phosphatase ≤2.5 times ULN or isolated elevations of transaminases or alkaline phosphatase up to 5 times ULN
**Elevated Baseline LFTs: AST and/or AL >1.5 times ULN concurrent with alkaline phosphatase >2.5 times ULN
***Febrile Neutropenia: ANC grade 4 with fever >38°C with intravenous antibiotics and/or hospitalization

Hematologic reactions

Reversible marrow suppression was the major dose-limiting toxicity of docetaxel [see Warnings and Precautions (5.3)]. The median time to nadir was 7 days, while the median duration of severe neutropenia (<500 cells/mm^3) was 7 days. Among 2045 patients with solid tumors and normal baseline LFTs, severe neutropenia occurred in 75.4% and lasted for more than 7 days in 2.9% of cycles.

Febrile neutropenia (<500 cells/mm^3 with fever >38°C with intravenous antibiotics and/or hospitalization) occurred in 11% of patients with solid tumors, in 12.3% of patients with metastatic breast cancer, and in 9.8% of 92 breast cancer patients premedicated with 3-day corticosteroids.

Severe infectious episodes occurred in 6.1% of patients with solid tumors, in 6.4% of patients with metastatic breast cancer, and in 5.4% of 92 breast cancer patients premedicated with 3-day corticosteroids.

Thrombocytopenia (<100,000 cells/mm^3) associated with fatal gastrointestinal hemorrhage has been reported.

Hypersensitivity reactions

Severe hypersensitivity reactions have been reported [see Boxed Warning, Warnings and Precautions (5.5)]. Minor events, including flushing, rash with or without pruritus, chest tightness, back pain, dyspnea, drug fever, or chills, have been reported and resolved after discontinuing the infusion and instituting appropriate therapy.

Fluid retention

Fluid retention can occur with the use of docetaxel [see Boxed Warning, Dosage and Administration (2.6), Warnings and Precautions (5.6)].

Cutaneous reactions

Severe skin toxicity is discussed elsewhere in the label [see Warnings and Precautions (5.8)]. Reversible cutaneous reactions characterized by a rash including localized eruptions, mainly on the feet and/or hands, but also on the arms, face, or thorax, usually associated with pruritus, have been observed. Eruptions generally occurred within 1 week after docetaxel infusion, recovered before the next infusion, and were not disabling.

Severe nail disorders were characterized by hypo or hyperpigmentation, and occasionally by onycholysis (in 0.8% of patients with solid tumors) and pain.

Neurologic reactions

Neurologic reactions are discussed elsewhere in the label [see Warnings and Precautions (5.9)].

Gastrointestinal reactions

Nausea, vomiting, and diarrhea were generally mild to moderate. Severe reactions occurred in 3%-5% of patients with solid tumors and to a similar extent among metastatic breast cancer patients. The incidence of severe reactions was 1% or less for the 92 breast cancer patients premedicated with 3-day corticosteroids.

Severe stomatitis occurred in 5.5% of patients with solid tumors, in 7.4% of patients with metastatic breast cancer, and in 1.1% of the 92 breast cancer patients premedicated with 3-day corticosteroids.

Cardiovascular reactions

Hypotension occurred in 2.8% of patients with solid tumors; 1.2% required treatment. Clinically meaningful events such as heart failure, sinus tachycardia, atrial flutter, dysrhythmia, unstable angina, pulmonary edema, and hypertension have occurred. Seven of 86 (8.1%) of metastatic breast cancer patients receiving docetaxel 100 mg/m^2 in a randomized trial and who had serial left ventricular ejection fractions assessed developed deterioration of LVEF by ≥10% associated with a drop below the institutional lower limit of normal.

Infusion site reactions

Infusion site reactions were generally mild and consisted of hyperpigmentation, inflammation, redness or dryness of the skin, phlebitis, extravasation, or swelling of the vein.

Hepatic reactions

In patients with normal LFTs at baseline, bilirubin values greater than the ULN occurred in 8.9% of patients. Increases in AST or ALT >1.5 times the ULN, or alkaline phosphatase >2.5 times ULN, were observed in 18.9% and 7.3% of patients, respectively. While on docetaxel, increases in AST and/or ALT >1.5 times ULN concomitant with alkaline phosphatase >2.5 times ULN occurred in 4.3% of patients with normal LFTs at baseline. Whether these changes were related to the drug or underlying disease has not been established.

Hematologic and other toxicity: Relation to dose and baseline liver chemistry abnormalities

Hematologic and other toxicity is increased at higher doses and in patients with elevated baseline liver function tests (LFTs). In the following tables, adverse drug reactions are compared for three populations: 730 patients with normal LFTs given docetaxel at 100 mg/m^2 in the randomized and single arm studies of metastatic breast cancer after failure of previous chemotherapy; 18 patients in these studies who had abnormal baseline LFTs (defined as AST and/or ALT >1.5 times ULN concurrent with alkaline phosphatase >2.5 times ULN); and 174 patients in Japanese studies given docetaxel at 60 mg/m^2 who had normal LFTs (see Tables 5 and 6).

Table 5: Hematologic Adverse Reactions in Breast Cancer Patients Previously Treated with Chemotherapy Treated at Docetaxel 100 mg/m^2 with Normal or Elevated Liver Function Tests or 60 mg/m^2 with Normal Liver Function Tests
Adverse Reaction | Docetaxel 100 mg/m^2 |  | Docetaxel 60 mg/m^2
Adverse Reaction | Normal LFTs* n=730 % | Elevated LFTs** n=18 % | Normal LFTs* n=174 %
Neutropenia
Any <2000 cells/mm^3 | 98 | 100 | 95
Grade 4 <500 cells/mm^3 | 84 | 94 | 75
Thrombocytopenia
Any <100,000 cells/mm^3 | 11 | 44 | 14
Grade 4 <20,000 cells/mm^3 | 1 | 17 | 1
Anemia <11 g/dL | 95 | 94 | 65
Infection***
Any | 23 | 39 | 1
Grade 3 and 4 | 7 | 33 | 0
Febrile Neutropenia****
By Patient | 12 | 33 | 0
By Course | 2 | 9 | 0
Septic Death | 2 | 6 | 1
Non-Septic Death | 1 | 11 | 0
*Normal Baseline LFTs: Transaminases ≤1.5 times ULN or alkaline phosphatase ≤2.5 times ULN or isolated elevations of transaminases or alkaline phosphatase up to 5 times ULN
**Elevated Baseline LFTs: AST and/or ALT>1.5 times ULN concurrent with alkaline phosphatase>2.5 times ULN
***Incidence of infection requiring hospitalization and/or intravenous antibiotics was 8.5% (n=62) among the 730 patients with normal LFTs at baseline; 7 patients had concurrent grade 3 neutropenia, and 46 patients had grade 4 neutropenia.
****Febrile Neutropenia: For 100 mg/m^2, ANC grade 4 and fever >38°C with intravenous antibiotics and/or hospitalization; for 60 mg/m^2, ANC grade 3/4 and fever >38.1°C

Table 6: Non-hematologic Adverse Reactions in Breast Cancer Patients Previously Treated with Chemotherapy Treated at Docetaxel 100 mg/m^2 with Normal or Elevated Liver Function Tests or 60 mg/m^2 with Normal Liver Function Tests
Adverse Reaction | Docetaxel 100 mg/m^2 |  | Docetaxel 60 mg/m^2
Adverse Reaction | Normal LFTs* n=730 % | Elevated LFTs** n=18 % | Normal LFTs* n=174 %
Acute Hypersensitivity
Reaction Regardless of Premedication
Any | 13 | 6 | 1
Severe | 1 | 0 | 0
Fluid Retention***
Regardless of Premedication
Any | 56 | 61 | 13
Severe | 8 | 17 | 0
Neurosensory
Any | 57 | 50 | 20
Severe | 6 | 0 | 0
Myalgia | 23 | 33 | 3
Cutaneous
Any | 45 | 61 | 31
Severe | 5 | 17 | 0
Asthenia
Any | 65 | 44 | 66
Severe | 17 | 22 | 0
Diarrhea
Any | 42 | 28 | NA
Severe | 6 | 11
Stomatitis
Any | 53 | 67 | 19
Severe | 8 | 39 | 1
*Normal Baseline LFTs: Transaminases ≤1.5 times ULN or alkaline phosphatase ≤2.5 times ULN or isolated elevations of transaminases or alkaline phosphatase up to 5 times ULN
**Elevated Baseline Liver Function: AST and/or ALT >1.5 times ULN concurrent with alkaline phosphatase >2.5 times ULN
***Fluid Retention includes (by COSTART): edema (peripheral, localized, generalized, lymphedema, pulmonary edema, and edema otherwise not specified) and effusion (pleural, pericardial, and ascites); no premedication given with the 60 mg/m^2 dose
NA = not available

In the three-arm monotherapy trial, TAX313, which compared docetaxel 60 mg/m^2, 75 mg/m^2 and 100 mg/m^2 in advanced breast cancer, grade 3/4 or severe adverse reactions occurred in 49.0% of patients treated with docetaxel 60 mg/m^2 compared to 55.3% and 65.9% treated with 75 mg/m^2 and 100 mg/m^2, respectively. Discontinuation due to adverse reactions was reported in 5.3% of patients treated with 60 mg/m^2 versus 6.9% and 16.5% for patients treated at 75 and 100 mg/m^2, respectively. Deaths within 30 days of last treatment occurred in 4.0% of patients treated with 60 mg/m^2 compared to 5.3% and 1.6% for patients treated at 75 mg/m^2 and 100 mg/m^2, respectively.

The following adverse reactions were associated with increasing docetaxel doses: fluid retention (26%, 38%, and 46% at 60 mg/m^2, 75 mg/m^2, and 100 mg/m^2, respectively), thrombocytopenia (7%, 11% and 12%, respectively), neutropenia (92%, 94%, and 97% respectively), febrile neutropenia (5%, 7%, and 14%, respectively), treatment-related grade 3/4 infection (2%, 3%, and 7%, respectively) and anemia (87%, 94%, and 97%, respectively).

Combination therapy with Docetaxel in the adjuvant treatment of breast cancer

The following table presents treatment-emergent adverse reactions observed in 744 patients, who were treated with docetaxel 75 mg/m^2 every 3 weeks in combination with doxorubicin and cyclophosphamide (see Table 7).

Table 7: Clinically Important Treatment-Emergent Adverse Reactions Regardless of Causal Relationship in Patients Receiving Docetaxel in Combination with Doxorubicin and Cyclophosphamide (TAX316).
 | Docetaxel 75 mg/m^2 + Doxorubicin 50 mg/m^2 + Cyclophosphamide 500 mg/m^2 (TAC) n=744 % |  | Fluorouracil 500 mg/m^2 + Doxorubicin 50 mg/m^2 + Cyclophosphamide 500 mg/m^2 (FAC) n=736 %
Adverse Reaction | Any | Grade 3/4 | Any | Grade 3/4
Anemia | 92 | 4 | 72 | 2
Neutropenia | 71 | 66 | 82 | 49
Fever in absence of infection | 47 | 1 | 17 | 0
Infection | 39 | 4 | 36 | 2
Thrombocytopenia | 39 | 2 | 28 | 1
Febrile neutropenia | 25 | N/A | 3 | N/A
Neutropenic infection | 12 | N/A | 6 | N/A
Hypersensitivity reactions | 13 | 1 | 4 | 0
Lymphedema | 4 | 0 | 1 | 0
Fluid Retention* | 35 | 1 | 15 | 0
Peripheral edema | 27 | 0 | 7 | 0
Weight gain | 13 | 0 | 9 | 0
Neuropathy sensory | 26 | 0 | 10 | 0
Neuro-cortical | 5 | 1 | 6 | 1
Neuropathy motor | 4 | 0 | 2 | 0
Neuro-cerebellar | 2 | 0 | 2 | 0
Syncope | 2 | 1 | 1 | 0
Alopecia | 98 | N/A | 97 | N/A
Skin toxicity | 27 | 1 | 18 | 0
Nail disorders | 19 | 0 | 14 | 0
Nausea | 81 | 5 | 88 | 10
Stomatitis | 69 | 7 | 53 | 2
Vomiting | 45 | 4 | 59 | 7
Diarrhea | 35 | 4 | 28 | 2
Constipation | 34 | 1 | 32 | 1
Taste perversion | 28 | 1 | 15 | 0
Anorexia | 22 | 2 | 18 | 1
Abdominal Pain | 11 | 1 | 5 | 0
Amenorrhea | 62 | N/A | 52 | N/A
Cough | 14 | 0 | 10 | 0
Cardiac dysrhythmias | 8 | 0 | 6 | 0
Vasodilatation | 27 | 1 | 21 | 1
Hypotension | 2 | 0 | 1 | 0
Phlebitis | 1 | 0 | 1 | 0
Asthenia | 81 | 11 | 71 | 6
Myalgia | 27 | 1 | 10 | 0
Arthralgia | 19 | 1 | 9 | 0
Lacrimation disorder | 11 | 0 | 7 | 0
Conjunctivitis | 5 | 0 | 7 | 0
* COSTART term and grading system for events related to treatment.

Of the 744 patients treated with TAC, 36.3% experienced severe treatment-emergent adverse reactions compared to 26.6% of the 736 patients treated with FAC. Dose reductions due to hematologic toxicity occurred in 1% of cycles in the TAC arm versus 0.1% of cycles in the FAC arm. Six percent of patients treated with TAC discontinued treatment due to adverse reactions, compared to 1.1% treated with FAC; fever in the absence of infection and allergy being the most common reasons for withdrawal among TAC-treated patients. Two patients died in each arm within 30 days of their last study treatment; 1 death per arm was attributed to study drugs.

Fever and infection

During the treatment period, fever in the absence of infection was seen in 46.5% of TAC-treated patients and in 17.1% of FAC-treated patients. Grade 3/4 fever in the absence of infection was seen in 1.3% and 0% of TAC and FAC-treated patients, respectively. Infection was seen in 39.4% of TAC-treated patients compared to 36.3% of FAC-treated patients. Grade 3/4 infection was seen in 3.9% and 2.2% of TAC-treated and FAC-treated patients, respectively. There were no septic deaths in either treatment arm during the treatment period.

Gastrointestinal reactions

In addition to gastrointestinal reactions reflected in the table above, 7 patients in the TAC arm were reported to have colitis/enteritis/large intestine perforation versus one patient in the FAC arm. Five of the 7 TAC-treated patients required treatment discontinuation; no deaths due to these events occurred during the treatment period.

Cardiovascular reactions

More cardiovascular reactions were reported in the TAC arm versus the FAC arm during the treatment period: arrhythmias, all grades (6.2% vs 4.9%), and hypotension, all grades (1.9% vs 0.8%). Twenty-six (26) patients (3.5%) in the TAC arm and 17 patients (2.3%) in the FAC arm developed CHF during the study period. All except one patient in each arm were diagnosed with CHF during the follow-up period. Two (2) patients in TAC arm and 4 patients in FAC arm died due to CHF. The risk of CHF was higher in the TAC arm in the first year, and then was similar in both treatment arms.

Adverse reactions during the follow-up period (median follow-up time of 8 years)

In study TAX316, the most common adverse reactions that started during the treatment period and persisted into the follow-up period in TAC and FAC patients are described below (median follow-up time of 8 years).

Nervous system disorders

In study TAX316, peripheral sensory neuropathy started during the treatment period and persisted into the follow-up period in 84 patients (11.3%) in TAC arm and 15 patients (2%) in FAC arm. At the end of the follow-up period (median follow-up time of 8 years), peripheral sensory neuropathy was observed to be ongoing in 10 patients (1.3%) in TAC arm, and in 2 patients (0.3%) in FAC arm.

Skin and subcutaneous tissue disorders

In study TAX316, alopecia persisting into the follow-up period after the end of chemotherapy was reported in 687 of 744 TAC patients (92.3%) and 645 of 736 FAC patients (87.6%). At the end of the follow-up period (actual median follow-up time of 8 years), alopecia was observed to be ongoing in 29 TAC patients (3.9%) and 16 FAC patients (2.2%).

Reproductive system and breast disorders

In study TAX316, amenorrhea that started during the treatment period and persisted into the follow-up period after the end of chemotherapy was reported in 202 of 744 TAC patients (27.2%) and 125 of 736 FAC patients (17.0%). Amenorrhea was observed to be ongoing at the end of the follow-up period (median follow-up time of 8 years) in 121 of 744 TAC patients (16.3%) and 86 FAC patients (11.7%).

General disorders and administration site conditions

In study TAX316, peripheral edema that started during the treatment period and persisted into the follow-up period after the end of chemotherapy was observed in 119 of 744 TAC patients (16.0%) and 23 of 736 FAC patients (3.1%). At the end of the follow-up period (actual median follow-up time of 8 years), peripheral edema was ongoing in 19 TAC patients (2.6%) and 4 FAC patients (0.5%).

In study TAX316, lymphedema that started during the treatment period and persisted into the follow-up period after the end of chemotherapy was reported in 11 of 744 TAC patients (1.5%) and 1 of 736 FAC patients (0.1%). At the end of the follow-up period (actual median follow-up time of 8 years), lymphedema was observed to be ongoing in 6 TAC patients (0.8%) and 1 FAC patient (0.1%).

In study TAX316, asthenia that started during the treatment period and persisted into the follow-up period after the end of chemotherapy was reported in 236 of 744 TAC patients (31.7%) and 180 of 736 FAC patients (24.5%). At the end of the follow-up period (actual median follow-up time of 8 years), asthenia was observed to be ongoing in 29 TAC patients (3.9%) and 16 FAC patients (2.2%).

Acute myeloid leukemia (AML)/Myelodysplastic syndrome (MDS)

AML occurred in the adjuvant breast cancer trial (TAX316). The cumulative risk of developing treatment-related AML at median follow-up time of 8 years in TAX316 was 0.4% for TAC-treated patients and 0.1% for FAC-treated patients. One TAC patient (0.1%) and 1 FAC patient (0.1%) died due to AML during the follow-up period (median follow-up time of 8 years).

Myelodysplastic syndrome occurred in 2 of 744 (0.3%) patients who received TAC and in 1 of 736 (0.1%) patients who received FAC. AML occurs at a higher frequency when these agents are given in combination with radiation therapy.

Lung Cancer

Monotherapy with docetaxel for unresectable, locally advanced or metastatic NSCLC previously treated with platinum-based chemotherapy

Docetaxel 75 mg/m^2: Treatment-emergent adverse drug reactions are shown in Table 8. Included in this table are safety data for a total of 176 patients with non-small cell lung carcinoma and a history of prior treatment with platinum-based chemotherapy who were treated in two randomized, controlled trials. These reactions were described using NCI Common Toxicity Criteria regardless of relationship to study treatment, except for the hematologic toxicities or where otherwise noted.

Table 8: Treatment-Emergent Adverse Reactions Regardless of Relationship to Treatment in Patients Receiving Docetaxel as Monotherapy for Non-small Cell Lung Cancer Previously Treated with Platinum-Based Chemotherapy*
Adverse Reaction | Docetaxel 75 mg/m^2 n=176 % | Best Supportive Care n=49 % | Vinorelbine/ Ifosfamide n=119 %
Neutropenia
Any | 84 | 14 | 83
Grade 3/4 | 65 | 12 | 57
Leukopenia
Any | 84 | 6 | 89
Grade 3/4 | 49 | 0 | 43
Thrombocytopenia
Any | 8 | 0 | 8
Grade 3/4 | 3 | 0 | 2
Anemia
Any | 91 | 55 | 91
Grade 3/4 | 9 | 12 | 14
Febrile Neutropenia** | 6 | NA† | 1
Infection
Any | 34 | 29 | 30
Grade 3/4 | 10 | 6 | 9
Treatment Related Mortality | 3 | NA† | 3
Hypersensitivity Reactions
Any | 6 | 0 | 1
Grade 3/4 | 3 | 0 | 0
Fluid Retention
Any | 34 | ND†† | 23
Severe | 3 |  | 3
Neurosensory
Any | 23 | 14 | 29
Grade 3/4 | 2 | 6 | 5
Neuromotor
Any | 16 | 8 | 10
Grade 3/4 | 5 | 6 | 3
Skin
Any | 20 | 6 | 17
Grade 3/4 | 1 | 2 | 1
Gastrointestinal
Nausea
Any | 34 | 31 | 31
Grade 3/4 | 5 | 4 | 8
Vomiting
Any | 22 | 27 | 22
Grade 3/4 | 3 | 2 | 6
Diarrhea
Any | 23 | 6 | 12
Grade 3/4 | 3 | 0 | 4
Alopecia | 56 | 35 | 50
Asthenia
Any | 53 | 57 | 54
Severe*** | 18 | 39 | 23
Stomatitis
Any | 26 | 6 | 8
Grade 3/4 | 2 | 0 | 1
Pulmonary
Any | 41 | 49 | 45
Grade 3/4 | 21 | 29 | 19
Nail Disorder
Any | 11 | 0 | 2
Severe*** | 1 | 0 | 0
Myalgia
Any | 6 | 0 | 3
Severe*** | 0 | 0 | 0
Arthralgia
Any | 3 | 2 | 2
Severe*** | 0 | 0 | 1
Taste Perversion
Any | 6 | 0 | 0
Severe*** | 1 | 0 | 0
*Normal Baseline LFTs: Transaminases ≤1.5 times ULN or alkaline phosphatase ≤2.5 times ULN or isolated
elevations of transaminases or alkaline phosphatase up to 5 times ULN
**Febrile Neutropenia: ANC grade 4 with fever >38°C with intravenous antibiotics and/or hospitalization
***COSTART term and grading system
†Not Applicable
††Not Done

Combination therapy with docetaxel in chemotherapy-naive advanced unresectable or metastatic NSCLC

Table 9 presents safety data from two arms of an open label, randomized controlled trial (TAX326) that enrolled patients with unresectable stage IIIB or IV non-small cell lung cancer and no history of prior chemotherapy. Adverse reactions were described using the NCI Common Toxicity Criteria except where otherwise noted.

Table 9: Adverse Reactions Regardless of Relationship to Treatment in Chemotherapy Naive Advanced Non-small Cell Lung Cancer Patients Receiving Docetaxel in Combination with Cisplatin
Adverse Reaction | Docetaxel 75 mg/m^2 + Cisplatin 75 mg/m^2 n=406 % | Vinorelbine 25 mg/m^2 + Cisplatin 100 mg/m^2 n=396 %
Neutropenia
Any | 91 | 90
Grade 3/4 | 74 | 78
Febrile Neutropenia | 5 | 5
Thrombocytopenia
Any | 15 | 15
Grade 3/4 | 3 | 4
Anemia
Any | 89 | 94
Grade 3/4 | 7 | 25
Infection
Any | 35 | 37
Grade 3/4 | 8 | 8
Fever in absence of infection
Any | 33 | 29
Grade 3/4 | <1 | 1
Hypersensitivity Reaction*
Any | 12 | 4
Grade 3/4 | 3 | <1
Fluid Retention**
Any | 54 | 42
All severe or life-threatening events | 2 | 2
Pleural effusion
Any | 23 | 22
All severe or life-threatening events | 2 | 2
Peripheral edema
Any | 34 | 18
All severe or life-threatening events | <1 | <1
Weight gain
Any | 15 | 9
All severe or life-threatening events | <1 | <1
Neurosensory
Any | 47 | 42
Grade 3/4 | 4 | 4
Neuromotor
Any | 19 | 17
Grade 3/4 | 3 | 6
Skin
Any | 16 | 14
Grade 3/4 | <1 | 1
Nausea
Any | 72 | 76
Grade 3/4 | 10 | 17
Vomiting
Any | 55 | 61
Grade 3/4 | 8 | 16
Diarrhea
Any | 47 | 25
Grade 3/4 | 7 | 3
Anorexia**
Any | 42 | 40
All severe or life-threatening events | 5 | 5
Stomatitis
Any | 24 | 21
Grade 3/4 | 2 | 1
Alopecia
Any | 75 | 42
Grade 3 | <1 | 0
Asthenia**
Any | 74 | 75
All severe or life-threatening events | 12 | 14
Nail Disorder**
Any | 14 | <1
All severe events | <1 | 0
Myalgia**
Any | 18 | 12
All severe events | <1 | <1
*Replaces NCI term "Allergy"
**COSTART term and grading system

Deaths within 30 days of last study treatment occurred in 31 patients (7.6%) in the docetaxel+cisplatin arm and 37 patients (9.3%) in the vinorelbine+cisplatin arm. Deaths within 30 days of last study treatment attributed to study drug occurred in 9 patients (2.2%) in the docetaxel+cisplatin arm and 8 patients (2.0%) in the vinorelbine+cisplatin arm.

The second comparison in the study, vinorelbine+cisplatin versus docetaxel+carboplatin (which did not demonstrate a superior survival associated with docetaxel [see Clinical Studies (14.3)]) demonstrated a higher incidence of thrombocytopenia, diarrhea, fluid retention, hypersensitivity reactions, skin toxicity, alopecia and nail changes on the docetaxel+carboplatin arm, while a higher incidence of anemia, neurosensory toxicity, nausea, vomiting, anorexia and asthenia was observed on the vinorelbine+cisplatin arm.

Prostate Cancer

Combination therapy with docetaxel in patients with prostate cancer

The following data are based on the experience of 332 patients, who were treated with docetaxel 75 mg/m^2 every 3 weeks in combination with prednisone 5 mg orally twice daily (see Table 10).

Table 10: Clinically Important Treatment-Emergent Adverse Reactions (Regardless of Relationship) in Patients with Prostate Cancer Who Received Docetaxel in Combination with Prednisone (TAX327)
 | Docetaxel 75 mg/m^2 every 3 weeks + prednisone 5 mg twice daily n=332 % |  | Mitoxantrone 12 mg/m^2 every 3 weeks + prednisone 5 mg twice daily n=335 %
Adverse Reaction | Any | Grade 3/4 | Any | Grade 3/4
Anemia | 67 | 5 | 58 | 2
Neutropenia | 41 | 32 | 48 | 22
Thrombocytopenia | 3 | 1 | 8 | 1
Febrile neutropenia | 3 | N/A | 2 | N/A
Infection | 32 | 6 | 20 | 4
Epistaxis | 6 | 0 | 2 | 0
Allergic Reactions | 8 | 1 | 1 | 0
Fluid Retention* | 24 | 1 | 5 | 0
Weight Gain* | 8 | 0 | 3 | 0
Peripheral Edema* | 18 | 0 | 2 | 0
Neuropathy Sensory | 30 | 2 | 7 | 0
Neuropathy Motor | 7 | 2 | 3 | 1
Rash/Desquamation | 6 | 0 | 3 | 1
Alopecia | 65 | N/A | 13 | N/A
Nail Changes | 30 | 0 | 8 | 0
Nausea | 41 | 3 | 36 | 2
Diarrhea | 32 | 2 | 10 | 1
Stomatitis/Pharyngitis | 20 | 1 | 8 | 0
Taste Disturbance | 18 | 0 | 7 | 0
Vomiting | 17 | 2 | 14 | 2
Anorexia | 17 | 1 | 14 | 0
Cough | 12 | 0 | 8 | 0
Dyspnea | 15 | 3 | 9 | 1
Cardiac left ventricular function | 10 | 0 | 22 | 1
Fatigue | 53 | 5 | 35 | 5
Myalgia | 15 | 0 | 13 | 1
Tearing | 10 | 1 | 2 | 0
Arthralgia | 8 | 1 | 5 | 1
*Related to treatment

Gastric Cancer

Combination therapy with docetaxel in gastric adenocarcinoma

Data in the following table are based on the experience of 221 patients with advanced gastric adenocarcinoma and no history of prior chemotherapy for advanced disease who were treated with docetaxel 75 mg/m^2 in combination with cisplatin and fluorouracil (see Table 11).

Table 11: Clinically Important Treatment-Emergent Adverse Reactions Regardless of Relationship to Treatment in the Gastric Cancer Study
 | Docetaxel 75 mg/m^2 + cisplatin 75 mg/m^2 + fluorouracil 750 mg/m^2 n=221 |  | Cisplatin 100 mg/m^2 + fluorouracil 1000 mg/m^2 n=224
Adverse Reaction | Any % | Grade 3/4 % | Any % | Grade 3/4 %
Anemia | 97 | 18 | 93 | 26
Neutropenia | 96 | 82 | 83 | 57
Fever in the absence of infection | 36 | 2 | 23 | 1
Thrombocytopenia | 26 | 8 | 39 | 14
Infection | 29 | 16 | 23 | 10
Febrile neutropenia | 16 | N/A | 5 | N/A
Neutropenic infection | 16 | N/A | 10 | N/A
Allergic reactions | 10 | 2 | 6 | 0
Fluid retention* | 15 | 0 | 4 | 0
Edema* | 13 | 0 | 3 | 0
Lethargy | 63 | 21 | 58 | 18
Neurosensory | 38 | 8 | 25 | 3
Neuromotor | 9 | 3 | 8 | 3
Dizziness | 16 | 5 | 8 | 2
Alopecia | 67 | 5 | 41 | 1
Rash/itch | 12 | 1 | 9 | 0
Nail changes | 8 | 0 | 0 | 0
Skin desquamation | 2 | 0 | 0 | 0
Nausea | 73 | 16 | 76 | 19
Vomiting | 67 | 15 | 73 | 19
Anorexia | 51 | 13 | 54 | 12
Stomatitis | 59 | 21 | 61 | 27
Diarrhea | 78 | 20 | 50 | 8
Constipation | 25 | 2 | 34 | 3
Esophagitis/dysphagia/odynophagia | 16 | 2 | 14 | 5
Gastrointestinal pain/cramping | 11 | 2 | 7 | 3
Cardiac dysrhythmias | 5 | 2 | 2 | 1
Myocardial ischemia | 1 | 0 | 3 | 2
Tearing | 8 | 0 | 2 | 0
Altered hearing | 6 | 0 | 13 | 2
Clinically important treatment-emergent adverse reactions were determined based upon frequency, severity, and clinical impact of the adverse reaction.
*Related to treatment

Head and Neck Cancer

Combination therapy with docetaxel in head and neck cancer

Table 12 summarizes the safety data obtained from patients that received induction chemotherapy with docetaxel 75 mg/m^2 in combination with cisplatin and fluorouracil followed by radiotherapy (TAX323; 174 patients) or chemoradiotherapy (TAX324; 251 patients). The treatment regimens are described in Section 14.6.

Table 12: Clinically Important Treatment-Emergent Adverse Reactions (Regardless of Relationship) in Patients with SCCHN Receiving Induction Chemotherapy with Docetaxel in Combination with Cisplatin and Fluorouracil Followed by Radiotherapy (TAX323) or Chemoradiotherapy (TAX324)
 | TAX323 (n=355) |  |  |  | TAX324 (n=494)
 | Docetaxel arm (n=174) |  | Comparator arm (n=181) |  | Docetaxel arm (n=251) |  | Comparator arm (n=243)
Adverse Reaction (by Body System) | Any % | Grade 3/4 % | Any % | Grade 3/4 % | Any % | Grade 3/4 % | Any % | Grade 3/4 %
Neutropenia | 93 | 76 | 87 | 53 | 95 | 84 | 84 | 56
Anemia | 89 | 9 | 88 | 14 | 90 | 12 | 86 | 10
Thrombocytopenia | 24 | 5 | 47 | 18 | 28 | 4 | 31 | 11
Infection | 27 | 9 | 26 | 8 | 23 | 6 | 28 | 5
Febrile neutropenia* | 5 | N/A | 2 | N/A | 12 | N/A | 7 | N/A
Neutropenic infection | 14 | N/A | 8 | N/A | 12 | N/A | 8 | N/A
Cancer pain | 21 | 5 | 16 | 3 | 17 | 9 | 20 | 11
Lethargy | 41 | 3 | 38 | 3 | 61 | 5 | 56 | 10
Fever in the absence of infection | 32 | 1 | 37 | 0 | 30 | 4 | 28 | 3
Myalgia | 10 | 1 | 7 | 0 | 7 | 0 | 7 | 2
Weight loss | 21 | 1 | 27 | 1 | 14 | 2 | 14 | 2
Allergy | 6 | 0 | 3 | 0 | 2 | 0 | 0 | 0
Fluid retention** | 20 | 0 | 14 | 1 | 13 | 1 | 7 | 2
Edema only | 13 | 0 | 7 | 0 | 12 | 1 | 6 | 1
Weight gain only | 6 | 0 | 6 | 0 | 0 | 0 | 1 | 0
Dizziness | 2 | 0 | 5 | 1 | 16 | 4 | 15 | 2
Neurosensory | 18 | 1 | 11 | 1 | 14 | 1 | 14 | 0
Altered hearing | 6 | 0 | 10 | 3 | 13 | 1 | 19 | 3
Neuromotor | 2 | 1 | 4 | 1 | 9 | 0 | 10 | 2
Alopecia | 81 | 11 | 43 | 0 | 68 | 4 | 44 | 1
Rash/itch | 12 | 0 | 6 | 0 | 20 | 0 | 16 | 1
Dry skin | 6 | 0 | 2 | 0 | 5 | 0 | 3 | 0
Desquamation | 4 | 1 | 6 | 0 | 2 | 0 | 5 | 0
Nausea | 47 | 1 | 51 | 7 | 77 | 14 | 80 | 14
Stomatitis | 43 | 4 | 47 | 11 | 66 | 21 | 68 | 27
Adverse Reaction (by Body System) | Any % | Grade 3/4 % | Any % | Grade 3/4 % | Any % | Grade 3/4 % | Any % | Grade 3/4 %
Vomiting | 26 | 1 | 39 | 5 | 56 | 8 | 63 | 10
Diarrhea | 33 | 3 | 24 | 4 | 48 | 7 | 40 | 3
Constipation | 17 | 1 | 16 | 1 | 27 | 1 | 38 | 1
Anorexia | 16 | 1 | 25 | 3 | 40 | 12 | 34 | 12
Esophagitis/dysphagia/ Odynophagia | 13 | 1 | 18 | 3 | 25 | 13 | 26 | 10
Taste, sense of smell altered | 10 | 0 | 5 | 0 | 20 | 0 | 17 | 1
Gastrointestinal pain/cramping | 8 | 1 | 9 | 1 | 15 | 5 | 10 | 2
Heartburn | 6 | 0 | 6 | 0 | 13 | 2 | 13 | 1
Gastrointestinal bleeding | 4 | 2 | 0 | 0 | 5 | 1 | 2 | 1
Cardiac dysrhythmia | 2 | 2 | 2 | 1 | 6 | 3 | 5 | 3
Venous*** | 3 | 2 | 6 | 2 | 4 | 2 | 5 | 4
Ischemia myocardial | 2 | 2 | 1 | 0 | 2 | 1 | 1 | 1
Tearing | 2 | 0 | 1 | 0 | 2 | 0 | 2 | 0
Conjunctivitis | 1 | 0 | 1 | 0 | 1 | 0 | 0.4 | 0
Clinically important treatment-emergent adverse reactions based upon frequency, severity, and clinical impact.
*Febrile neutropenia: grade ≥2 fever concomitant with grade 4 neutropenia requiring intravenous antibiotics and/or hospitalization.
**Related to treatment.
***Includes superficial and deep vein thrombosis and pulmonary embolism

6.2 Postmarketing Experience

The following adverse reactions have been identified from clinical trials and/or postmarketing surveillance. Because these reactions are reported from a population of uncertain size, it is not always possible to reliably estimate their frequency or establish a causal relationship to drug exposure.

Body as a whole: diffuse pain, chest pain, radiation recall phenomenon, injection site recall reaction (recurrence of skin reaction at a site of previous extravasation following administration of docetaxel at a different site) at the site of previous extravasation.

Cardiovascular: atrial fibrillation, deep vein thrombosis, ECG abnormalities, thrombophlebitis, pulmonary embolism, syncope, tachycardia, myocardial infarction. Ventricular arrhythmia, including ventricular tachycardia, in patients treated with docetaxel in combination regimens including doxorubicin, 5-fluorouracil and/or cyclophosphamide may be associated with fatal outcome.

Cutaneous: cutaneous lupus erythematosus, bullous eruptions such as erythema multiforme and severe cutaneous adverse reactions (SCARs) such as Stevens-Johnson syndrome, toxic epidermal necrolysis and acute generalized exanthematous pustulosis, scleroderma-like changes (usually preceded by peripheral lymphedema), severe palmar-plantar erythrodysesthesia, and permanent alopecia.

Gastrointestinal: enterocolitis, including colitis, ischemic colitis, and neutropenic enterocolitis, which may be fatal. Abdominal pain, anorexia, constipation, duodenal ulcer, esophagitis, gastrointestinal hemorrhage, gastrointestinal perforation, intestinal obstruction, ileus, and dehydration as a consequence of gastrointestinal events.

Hearing: ototoxicity, hearing disorders and/or hearing loss, including during use with other ototoxic drugs.

Hematologic: bleeding episodes, disseminated intravascular coagulation (DIC), often in association with sepsis or multiorgan failure.

Hepatic: hepatitis, sometimes fatal, primarily in patients with pre-existing liver disorders.

Hypersensitivity: anaphylactic shock with fatal outcome in patients who received premedication. Severe hypersensitivity reactions with fatal outcome with docetaxel in patients who previously experienced hypersensitivity reactions to paclitaxel.

Metabolism and nutrition disorders: electrolyte imbalance, including hyponatremia, hypokalemia, hypomagnesemia, and hypocalcemia. Tumor lysis syndrome, sometimes fatal. Neurologic: confusion, seizures or transient loss of consciousness, sometimes appearing during the infusion of the drug.

Ophthalmologic: conjunctivitis, lacrimation or lacrimation with or without conjunctivitis, cystoid macular edema (CME). Excessive tearing which may be attributable to lacrimal duct obstruction. Transient visual disturbances (flashes, flashing lights, scotomata), typically occurring during drug infusion and reversible upon discontinuation of the infusion, in association with hypersensitivity reactions.

Respiratory: dyspnea, acute pulmonary edema, acute respiratory distress syndrome/pneumonitis, interstitial lung disease, interstitial pneumonia, respiratory failure, and pulmonary fibrosis, which may be fatal. Radiation pneumonitis in patients receiving concomitant radiotherapy.

Renal: renal insufficiency and renal failure, the majority of cases were associated with concomitant nephrotoxic drugs.

Second primary malignancies: second primary malignancies, including AML, MDS, NHL, and renal cancer [see Warnings and Precautions (5.7)].

Musculoskeletal disorder: myositis.

7 DRUG INTERACTIONS

Docetaxel is a CYP3A4 substrate. In vitro studies have shown that the metabolism of docetaxel may be modified by the concomitant administration of compounds that induce, inhibit, or are metabolized by cytochrome P450 3A4.

In vivo studies showed that the exposure of docetaxel increased 2.2-fold when it was coadministered with ketoconazole, a potent inhibitor of CYP3A4. Protease inhibitors, particularly ritonavir, may increase the exposure of docetaxel. Concomitant use of BEIZRAY and drugs that inhibit CYP3A4 may increase exposure to docetaxel and should be avoided. In patients receiving treatment with BEIZRAY, close monitoring for toxicity and a BEIZRAY dose reduction could be considered if systemic administration of a potent CYP3A4 inhibitor cannot be avoided [see Dosage and Administration (2.7), Clinical Pharmacology (12.3)].

8 USE IN SPECIFIC POPULATIONS

8.1 Pregnancy

Risk Summary

Based on findings in animal reproduction studies and its mechanism of action, BEIZRAY can cause fetal harm when administered to a pregnant woman [see Clinical Pharmacology (12.1)]. Available data from case reports in the literature and pharmacovigilance with docetaxel use in pregnant women are not sufficient to inform the drug-associated risk of major birth defects, miscarriage, or adverse maternal or fetal outcomes. BEIZRAY contains alcohol which can interfere with neurobehavioral development [see Clinical Considerations]. In animal reproductive studies, administration of docetaxel to pregnant rats and rabbits during the period of organogenesis caused an increased incidence of embryo-fetal toxicities, including intrauterine mortality, at doses as low as 0.02 and 0.003 times the recommended human dose based on body surface area, respectively [see Data]. Advise pregnant women and females of reproductive potential of the potential risk to a fetus.

The estimated background risk of major birth defects and miscarriage for the indicated populations is unknown. All pregnancies have a background risk of birth defect, miscarriage, or other adverse outcomes. In the U.S. general population, the estimated background risk of major birth defects and miscarriage in clinically recognized pregnancies is 2% to 4% and 15% to 20%, respectively.

Clinical Considerations

BEIZRAY contains alcohol [see Warnings and Precautions (5.13)]. Published studies have demonstrated that alcohol is associated with fetal harm including central nervous system abnormalities, behavioral disorders, and impaired intellectual development.

Data

Animal data

Intravenous administration of ≥ 0.3 and 0.03 mg/kg/day docetaxel to pregnant rats and rabbits, respectively, during the period of organogenesis caused an increased incidence of intrauterine mortality, resorptions, reduced fetal weights, and fetal ossification delays. Maternal toxicity was also observed at these doses, which were approximately 0.02 and 0.003 times the daily maximum recommended human dose based on body surface area, respectively.

8.2 Lactation

Risk Summary

There is no information regarding the presence of docetaxel in human milk, or on its effects on milk production or the breastfed child. No lactation studies in animals have been conducted. Because of the potential for serious adverse reactions in a breastfed child, advise women not to breastfeed during treatment with BEIZRAY and for 1 week after the last dose.

8.3 Females and Males of Reproductive Potential

Based on findings in animals, BEIZRAY can cause fetal harm when administered to a pregnant woman [see Use in Specific Populations (8.1)].

Pregnancy Testing

Verify pregnancy status in females of reproductive potential prior to initiating BEIZRAY.

Contraception

Females

Based on genetic toxicity findings, advise females of reproductive potential to use effective contraception during treatment and for 2 months after the last dose of BEIZRAY.

Males

Based on genetic toxicity findings, advise male patients with female partners of reproductive potential to use effective contraception during treatment and for 4 months after the last dose of BEIZRAY.

Infertility

Based on findings in animal studies, BEIZRAY may impair fertility in males of reproductive potential [see Nonclinical Toxicology (13.1)].

8.4 Pediatric Use

The alcohol content of BEIZRAY Injection should be taken into account when given to pediatric patients [see Warnings and Precautions (5.13)].

The efficacy of BEIZRAY in pediatric patients as monotherapy or in combination has not been established. The overall safety profile of BEIZRAY in pediatric patients receiving monotherapy or TCF was consistent with the known safety profile in adults.

Docetaxel has been studied in a total of 289 pediatric patients: 239 in 2 trials with monotherapy and 50 in combination treatment with cisplatin and 5-fluorouracil (TCF).

Docetaxel Monotherapy

Docetaxel monotherapy was evaluated in a dose-finding phase 1 trial in 61 pediatric patients (median age 12.5 years, range 1-22 years) with a variety of refractory solid tumors. The recommended dose was 125 mg/m^2 as a 1-hour intravenous infusion every 21 days. The primary dose limiting toxicity was neutropenia.

The recommended dose for docetaxel monotherapy was evaluated in a phase 2 single-arm trial in 178 pediatric patients (median age 12 years, range 1-26 years) with a variety of recurrent/refractory solid tumors. Efficacy was not established with tumor response rates ranging from one complete response (CR) (0.6%) in a patient with undifferentiated sarcoma to four partial responses (2.2%) seen in one patient each with Ewing Sarcoma, neuroblastoma, osteosarcoma, and squamous cell carcinoma.

Docetaxel in Combination

Docetaxel was studied in combination with cisplatin and 5-fluorouracil (TCF) versus cisplatin and 5-fluorouracil (CF) for the induction treatment of nasopharyngeal carcinoma (NPC) in pediatric patients prior to chemoradiation consolidation. Seventy-five patients (median age 16 years, range 9 to 21 years) were randomized (2:1) to docetaxel (75 mg/m^2) in combination with cisplatin (75 mg/m^2) and 5-fluorouracil (750 mg/m^2) (TCF) or to cisplatin (80 mg/m^2) and 5-fluorouracil (1000 mg/m^2/day) (CF). The primary endpoint was the CR rate following induction treatment of NPC. One patient out of 50 in the TCF group (2%) had a complete response while none of the 25 patients in the CF group had a complete response.

Pharmacokinetics

Pharmacokinetic parameters for docetaxel were determined in 2 pediatric solid tumor trials. Following docetaxel administration at 55 mg/m^2 to 235 mg/m^2 in a 1-hour intravenous infusion every 3 weeks in 25 patients aged 1 to 20 years (median 11 years), docetaxel clearance was 17.3±10.9 L/h/m^2.

Docetaxel was administered in combination with cisplatin and 5-fluorouracil (TCF), at dose levels of 75 mg/m2 in a 1-hour intravenous infusion day 1 in 28 patients aged 10 to 21 years (median 16 years, 17 patients were older than 16). Docetaxel clearance was 17.9±8.75 L/h/m2, corresponding to an AUC of 4.20±2.57 μg∙h/mL.

In summary, the body surface area adjusted clearance of docetaxel monotherapy and TCF combination in children were comparable to those in adults [see Clinical Pharmacology (12.3)].

8.5 Geriatric Use

In general, dose selection for an elderly patient should be cautious, reflecting the greater frequency of decreased hepatic, renal, or cardiac function and of concomitant disease or other drug therapy in elderly patients.

Non-small Cell Lung Cancer

In a study conducted in chemotherapy-naive patients with NSCLC (TAX326), 148 patients (36%) in the docetaxel+cisplatin group were 65 years of age or greater. There were 128 patients (32%) in the vinorelbine+cisplatin group 65 years of age or greater. In the docetaxel+cisplatin group, patients less than 65 years of age had a median survival of 10.3 months (95% CI: 9.1 months, 11.8 months) and patients 65 years or older had a median survival of 12.1 months (95% CI: 9.3 months, 14 months). In patients 65 years of age or greater treated with docetaxel+cisplatin, diarrhea (55%), peripheral edema (39%) and stomatitis (28%) were observed more frequently than in the vinorelbine+cisplatin group (diarrhea 24%, peripheral edema 20%, stomatitis 20%). Patients treated with docetaxel+cisplatin who were 65 years of age or greater were more likely to experience diarrhea (55%), infections (42%), peripheral edema (39%) and stomatitis (28%) compared to patients less than the age of 65 administered the same treatment (43%, 31%, 31% and 21%, respectively).

When docetaxel was combined with carboplatin for the treatment of chemotherapy-naive, advanced non-small cell lung carcinoma, patients 65 years of age or greater (28%) experienced higher frequency of infection compared to similar patients treated with docetaxel+cisplatin, and a higher frequency of diarrhea, infection and peripheral edema than elderly patients treated with vinorelbine+cisplatin.

Prostate Cancer

Of the 333 patients treated with docetaxel every three weeks plus prednisone in the prostate cancer study (TAX327), 209 patients were 65 years of age or greater and 68 patients were older than 75 years. In patients treated with docetaxel every three weeks, the following treatment-emergent adverse reactions occurred at rates ≥10% higher in patients 65 years of age or greater compared to younger patients: anemia (71% vs 59%), infection (37% vs 24%), nail changes (34% vs 23%), anorexia (21% vs 10%), weight loss (15% vs 5%), respectively.

Breast Cancer

In the adjuvant breast cancer trial (TAX316), docetaxel in combination with doxorubicin and cyclophosphamide was administered to 744 patients of whom 48 (6%) were 65 years of age or greater. The number of elderly patients who received this regimen was not sufficient to determine whether there were differences in safety and efficacy between elderly and younger patients.

Gastric Cancer

Among the 221 patients treated with docetaxel in combination with cisplatin and fluorouracil in the gastric cancer study, 54 were 65 years of age or older and 2 patients were older than 75 years. In this study, the number of patients who were 65 years of age or older was insufficient to determine whether they respond differently from younger patients. However, the incidence of serious adverse reactions was higher in the elderly patients compared to younger patients. The incidence of the following adverse reactions (all grades, regardless of relationship): lethargy, stomatitis, diarrhea, dizziness, edema, febrile neutropenia/neutropenic infection occurred at rates ≥10% higher in patients who were 65 years of age or older compared to younger patients. Elderly patients treated with TCF should be closely monitored.

Head and Neck Cancer

Among the 174 and 251 patients who received the induction treatment with docetaxel in combination with cisplatin and fluorouracil (TPF) for SCCHN in the TAX323 and TAX324 studies, 18 (10%) and 32 (13%) of the patients were 65 years of age or older, respectively. These clinical studies of docetaxel in combination with cisplatin and fluorouracil in patients with SCCHN did not include sufficient numbers of patients aged 65 and over to determine whether they respond differently from younger patients. Other reported clinical experience with this treatment regimen has not identified differences in responses between elderly and younger patients.

8.6 Hepatic Impairment

Avoid BEIZRAY in patients with bilirubin >ULN and patients with AST and/or ALT >1.5 × ULN concomitant with alkaline phosphatase >2.5 × ULN [see Boxed Warning, Warnings and Precautions (5.2), Clinical Pharmacology (12.3)].

The alcohol content of BEIZRAY Injection should be taken into account when given to patients with hepatic impairment [see Warnings and Precautions (5.13)].

10 OVERDOSAGE

There is no known antidote for BEIZRAY overdosage. In case of overdosage, the patient should be kept in a specialized unit where vital functions can be closely monitored. Anticipated complications of overdosage include: bone marrow suppression, peripheral neurotoxicity, and mucositis. Patients should receive therapeutic G-CSF as soon as possible after discovery of overdose. Other appropriate symptomatic measures should be taken, as needed.

In two reports of overdose, one patient received 150 mg/m^2 and the other received 200 mg/m^2 as 1-hour infusions. Both patients experienced severe neutropenia, mild asthenia, cutaneous reactions, and mild paresthesia, and recovered without incident.

In mice, lethality was observed following single intravenous doses that were ≥154 mg/kg (about 4.5 times the human dose of 100 mg/m^2 on a mg/m^2 basis); neurotoxicity associated with paralysis, non-extension of hind limbs, and myelin degeneration was observed in mice at 48 mg/kg (about 1.5 times the human dose of 100 mg/m^2 basis). In male and female rats, lethality was observed at a dose of 20 mg/kg (comparable to the human dose of 100 mg/m^2 on a mg/m^2 basis) and was associated with abnormal mitosis and necrosis of multiple organs.

11 DESCRIPTION

Docetaxel is an antineoplastic agent belonging to the taxoid family. The chemical name for docetaxel is (2R,3S)-N-carboxy-3-phenylisoserine,N-tert-butyl ester, 13-ester with 5β, 20-epoxy-1,2α,4,7β,10β,13α-hex-ahydroxytax-11-en-9-one 4-acetate 2-benzoate. Docetaxel has the following structural formula:

Docetaxel is a white to almost-white powder with an empirical formula of C43H53NO14, and a molecular weight of 807.89. It is highly lipophilic and practically insoluble in water.

BEIZRAY Injection for intravenous use is a sterile, non-pyrogenic, clear colorless liquid at 20 mg/mL concentration. Each mL contains 20 mg docetaxel (anhydrous) in 0.770 grams dehydrated alcohol (100% v/v) solution, with citric acid for pH adjustment.

The BEIZRAY kit also contains a single dose vial of IV Solution Stabilizer, 50 mL of 25% Albumin Human USP solution.

25% Albumin Human USP is a clear, slightly viscous liquid; it is almost colorless or slightly yellow or green. The product contains 0.25 g Albumin Human USP per mL and is stabilized with 0.08 mmol sodium acetyltryptophanate and 0.08 mmol sodium caprylate per gram of albumin.

12 CLINICAL PHARMACOLOGY

12.1 Mechanism of Action

Docetaxel is an antineoplastic agent that acts by disrupting the microtubular network in cells that is essential for mitotic and interphase cellular functions. Docetaxel binds to free tubulin and promotes the assembly of tubulin into stable microtubules while simultaneously inhibiting their disassembly. This leads to the production of microtubule bundles without normal function and to the stabilization of microtubules, which results in the inhibition of mitosis in cells. Docetaxel's binding to microtubules does not alter the number of protofilaments in the bound microtubules, a feature which differs from most spindle poisons currently in clinical use.

12.2 Pharmacodynamics

Docetaxel exposure-response relationships and the time course of pharmacodynamic response are unknown.

12.3 Pharmacokinetics

Absorption

The pharmacokinetics of docetaxel has been evaluated in cancer patients after administration of 20 mg/m^2 to 115 mg/m^2 in phase 1 studies. The area under the curve (AUC) was dose proportional following doses of 70 mg/m^2 to 115 mg/m^2 with infusion times of 1 to 2 hours.

Docetaxel's pharmacokinetic profile is consistent with a three-compartment pharmacokinetic model, with initial rapid distribution phase and the late (terminal) phase.

Distribution

Mean steady state volume of distribution was 113 L. Docetaxel is approximately 94% protein bound in vitro, mainly to α1-acid glycoprotein, albumin, and lipoproteins. In three cancer patients, the in vitro binding to plasma proteins was approximately 97%. Dexamethasone does not affect the protein binding of docetaxel.

Elimination

With extended plasma sampling up to 8 to 22 days post infusion, the estimated mean total body clearance was 18 L/h/m^2 (range of means: 14 to 23) and mean terminal elimination half-life was 116 hours (range of means: 92 to 135).

Metabolism

Docetaxel is metabolized by the CYP3A4 isoenzyme in vitro [see Drug Interactions (7)].

Excretion

In three cancer patients urinary and fecal excretion accounted for approximately 6% and 75% of the administered radioactivity, respectively, within 7 days. About 80% of the radioactivity recovered in feces was excreted during the first 48 hours as 1 major and 3 minor metabolites with less than 8% as unchanged drug.

Specific Populations

Effect of Age: A population pharmacokinetic analysis was carried out after docetaxel treatment of 535 patients dosed at 100 mg/m^2. Pharmacokinetic parameters estimated by this analysis were very close to those estimated from phase 1 studies. The pharmacokinetics of docetaxel was not influenced by age.

Effect of Gender: The population pharmacokinetics analysis described above also indicated that gender did not influence the pharmacokinetics of docetaxel.

Hepatic Impairment: The population pharmacokinetic analysis described above indicated that in patients with clinical chemistry data suggestive of mild to moderate liver impairment (AST and/or ALT >1.5 times ULN concomitant with alkaline phosphatase >2.5 times ULN), total body clearance was lowered by an average of 27%, resulting in a 38% increase in systemic exposure (AUC). This average, however, includes a substantial range and there is, at present, no measurement that would allow recommendation for dose adjustment in such patients. Patients with combined abnormalities of transaminase and alkaline phosphatase should not be treated with docetaxel. Patients with severe hepatic impairment have not been studied [see Warnings and Precautions (5.2), Use in Specific Populations (8.6)].

Effect of Race: Mean total body clearance for Japanese patients dosed at the range of 10 mg/m^2 to 90 mg/m^2 was similar to that of European/American populations dosed at 100 mg/m^2, suggesting no significant difference in the elimination of docetaxel in the two populations.

Drug Interaction Studies

Effect of Ketoconazole: The effect of ketoconazole (a strong CYP3A4 inhibitor) on the pharmacokinetics of docetaxel was investigated in 7 cancer patients. Patients were randomized to receive either docetaxel (100 mg/m^2 intravenous) alone or docetaxel (10 mg/m^2 intravenous) in combination with ketoconazole (200 mg orally once daily for 3 days) in a crossover design with a 3-week washout period. The results of this study indicated that the mean dose-normalized AUC of docetaxel was increased 2.2-fold and its clearance was reduced by 49% when docetaxel was coadministered with ketoconazole [see Dosage and Administration (2.7), Drug Interactions (7)].

Effect of combination therapies

- Dexamethasone: Docetaxel total body clearance was not modified by pretreatment with dexamethasone.
- Cisplatin: Clearance of docetaxel in combination therapy with cisplatin was similar to that previously observed following monotherapy with docetaxel. The pharmacokinetic profile of cisplatin in combination therapy with docetaxel was similar to that observed with cisplatin alone.
- Cisplatin and Fluorouracil: The combined administration of docetaxel, cisplatin and fluorouracil in 12 patients with solid tumors had no influence on the pharmacokinetics of each individual drug.
- Prednisone: A population pharmacokinetic analysis of plasma data from 40 patients with metastatic castration-resistant prostate cancer indicated that docetaxel systemic clearance in combination with prednisone is similar to that observed following administration of docetaxel alone.
- Cyclophosphamide and Doxorubicin: A study was conducted in 30 patients with advanced breast cancer to determine the potential for drug-drug interactions between docetaxel (75 mg/m^2), doxorubicin (50 mg/m^2), and cyclophosphamide (500 mg/m^2) when administered in combination. The coadministration of docetaxel had no effect on the pharmacokinetics of doxorubicin and cyclophosphamide when the three drugs were given in combination compared to coadministration of doxorubicin and cyclophosphamide only. In addition, doxorubicin and cyclophosphamide had no effect on docetaxel plasma clearance when the three drugs were given in combination compared to historical data for docetaxel monotherapy.

13 NONCLINICAL TOXICOLOGY

13.1 Carcinogenesis, Mutagenesis, Impairment of Fertility

Carcinogenicity studies with docetaxel have not been performed.

Docetaxel was genotoxic by an aneugenic mechanism in the in vitro chromosome aberration test in CHO-K1 cells and in the in vivo micronucleus test in mice administered doses of 0.39 to 1.56 mg/kg (about 1/60th to 1/15th the recommended human dose on a mg/m^2 basis). Docetaxel was not mutagenic in the Ames test or the CHO/HGPRT gene mutation assays.

Docetaxel did not reduce fertility in rats when administered in multiple intravenous doses of up to 0.3 mg/kg (about 1/50th the recommended human dose on a mg/m^2 basis), but decreased testicular weights were reported. This correlates with findings of a 10-cycle toxicity study (dosing once every 21 days for 6 months) in rats and dogs in which testicular atrophy or degeneration was observed at intravenous doses of 5 mg/kg in rats and 0.375 mg/kg in dogs (about 1/3rd and 1/15th the recommended human dose on a mg/m^2 basis, respectively). An increased frequency of dosing in rats produced similar effects at lower dose levels.

14 CLINICAL STUDIES

14.1 Locally Advanced or Metastatic Breast Cancer

The efficacy and safety of docetaxel have been evaluated in locally advanced or metastatic breast cancer after failure of previous chemotherapy (alkylating agent–containing regimens or anthracycline-containing regimens).

Randomized Trials

In one randomized trial, patients with a history of prior treatment with an anthracycline-containing regimen were assigned to treatment with docetaxel (100 mg/m^2 every 3 weeks) or the combination of mitomycin (12 mg/m^2 every 6 weeks) and vinblastine (6 mg/m^2 every 3 weeks). Two hundred three patients were randomized to docetaxel and 189 to the comparator arm. Most patients had received prior chemotherapy for metastatic disease; only 27 patients on the docetaxel arm and 33 patients on the comparator arm entered the study following relapse after adjuvant therapy. Three-quarters of patients had measurable, visceral metastases. The primary endpoint was time to progression. The following table summarizes the study results. (See Table 13.)

Table 13: Efficacy of Docetaxel in the Treatment of Breast Cancer Patients Previously Treated with an Anthracycline-Containing Regimen (Intent-to-Treat Analysis)
Efficacy Parameter | Docetaxel (n=203) | Mitomycin/ Vinblastine (n=189) | p-value
Median Survival | 11.4 months | 8.7 months | p=0.01 Log Rank
Risk Ratio*, Mortality (Docetaxel: Control) | 0.73 |  | p=0.01 Log Rank
95% CI (Risk Ratio) | 0.58-0.93 |  | p=0.01 Log Rank
Median Time to Progression | 4.3 months | 2.5 months | p=0.01 Log Rank
Risk Ratio*, Progression (Docetaxel: Control) | 0.75 |  | p=0.01 Log Rank
95% CI (Risk Ratio) | 0.61-0.94 |  | p=0.01 Log Rank
Overall Response Rate | 28.1% | 9.5% | p<0.0001 Chi Square
Complete Response Rate | 3.4% | 1.6% | p<0.0001 Chi Square
*For the risk ratio, a value less than 1.00 favors docetaxel.

In a second randomized trial, patients previously treated with an alkylating-containing regimen were assigned to treatment with docetaxel (100 mg/m^2) or doxorubicin (75 mg/m^2) every 3 weeks. One hundred sixty-one patients were randomized to docetaxel and 165 patients to doxorubicin. Approximately one-half of patients had received prior chemotherapy for metastatic disease, and one-half entered the study following relapse after adjuvant therapy. Three-quarters of patients had measurable, visceral metastases. The primary endpoint was time to progression. The study results are summarized below. (See Table 14.)

Table 14: Efficacy of Docetaxel in the Treatment of Breast Cancer Patients Previously Treated with an Alkylating-Containing Regimen (Intent-to-Treat Analysis)
Efficacy Parameter | Docetaxel (n=161) | Doxorubicin (n=165) | p-value
Median Survival | 14.7 months | 14.3 months | p=0.39 Log Rank
Risk Ratio*, Mortality (Docetaxel: Control) | 0.89 |  | p=0.39 Log Rank
95% CI (Risk Ratio) | 0.68-1.16 |  | p=0.39 Log Rank
Median Time to Progression | 6.5 months | 5.3 months | p=0.45 Log Rank
Risk Ratio*, Progression (Docetaxel: Control) | 0.93 |  | p=0.45 Log Rank
95% CI (Risk Ratio) | 0.71-1.16 |  | p=0.45 Log Rank
Overall Response Rate | 45.3% | 29.7% | p=0.004 Chi Square
Complete Response Rate | 6.8% | 4.2% | p=0.004 Chi Square

*For the risk ratio, a value less than 1.00 favors docetaxel.

In another multicenter open-label, randomized trial (TAX313), in the treatment of patients with advanced breast cancer who progressed or relapsed after one prior chemotherapy regimen, 527 patients were randomized to receive docetaxel monotherapy 60 mg/m^2 (n=151), 75 mg/m^2 (n=188) or 100 mg/m^2 (n=188). In this trial, 94% of patients had metastatic disease and 79% had received prior anthracycline therapy. Response rate was the primary endpoint. Response rates increased with docetaxel dose: 19.9% for the 60 mg/m^2 group compared to 22.3% for the 75 mg/m^2 and 29.8% for the 100 mg/m^2 group; pair-wise comparison between the 60 mg/m^2 and 100 mg/m^2 groups was statistically significant (p=0.037).

Single Arm Studies

Docetaxel at a dose of 100 mg/m^2 was studied in six single arm studies involving a total of 309 patients with metastatic breast cancer in whom previous chemotherapy had failed. Among these, 190 patients had anthracycline-resistant breast cancer, defined as progression during an anthracycline-containing chemotherapy regimen for metastatic disease, or relapse during an anthracycline-containing adjuvant regimen. In anthracycline-resistant patients, the overall response rate was 37.9% (72/190; 95% CI: 31.0-44.8) and the complete response rate was 2.1%.

Docetaxel was also studied in three single arm Japanese studies at a dose of 60 mg/m^2, in 174 patients who had received prior chemotherapy for locally advanced or metastatic breast cancer. Among 26 patients whose best response to an anthracycline had been progression, the response rate was 34.6% (95% CI: 17.2-55.7), similar to the response rate in single arm studies of 100 mg/m^2.

14.2 Adjuvant Treatment of Breast Cancer

A multicenter, open-label, randomized trial (TAX316) evaluated the efficacy and safety of docetaxel for the adjuvant treatment of patients with axillary-node-positive breast cancer and no evidence of distant metastatic disease. After stratification according to the number of positive lymph nodes (1-3, 4+), 1491 patients were randomized to receive either docetaxel 75 mg/m^2 administered 1-hour after doxorubicin 50 mg/m^2 and cyclophosphamide 500 mg/m^2 (TAC arm), or doxorubicin 50 mg/m^2 followed by fluorouracil 500 mg/m^2 and cyclophosphamide 500 mg/m^2 (FAC arm). Both regimens were administered every 3 weeks for 6 cycles. Docetaxel was administered as a 1-hour infusion; all other drugs were given as intravenous bolus on day 1. In both arms, after the last cycle of chemotherapy, patients with positive estrogen and/or progesterone receptors received tamoxifen 20 mg daily for up to 5 years. Adjuvant radiation therapy was prescribed according to guidelines in place at participating institutions and was given to 69% of patients who received TAC and 72% of patients who received FAC.

Results from a second interim analysis (median follow-up 55 months) are as follows: In study TAX316, the docetaxel-containing combination regimen TAC showed significantly longer disease-free survival (DFS) than FAC (hazard ratio=0.74; 2-sided 95% CI=0.60, 0.92, stratified log rank p=0.0047). The primary endpoint, disease-free survival, included local and distant recurrences, contralateral breast cancer and deaths from any cause. The overall reduction in risk of relapse was 25.7% for TAC-treated patients. (See Figure 1.)

At the time of this interim analysis, based on 219 deaths, overall survival was longer for TAC than FAC (hazard ratio=0.69, 2-sided 95% CI=0.53, 0.90). (See Figure 2.) There will be further analysis at the time survival data mature.

Figure 1: TAX316 Disease Free Survival K-M curve

Figure 2: TAX316 Overall Survival K-M Curve

The following table describes the results of subgroup analyses for DFS and OS (see Table 15).

Table 15: Subset Analyses-Adjuvant Breast Cancer Study
Patient subset | Number of patients | Disease Free Survival |  | Overall Survival
Patient subset | Number of patients | Hazard ratio* | 95% CI | Hazard ratio* | 95% CI
No. of positive nodes
Overall | 744 | 0.74 | (0.60, 0.92) | 0.69 | (0.53, 0.90)
1-3 | 467 | 0.64 | (0.47, 0.87) | 0.45 | (0.29, 0.70)
4+ | 277 | 0.84 | (0.63, 1.12) | 0.93 | (0.66, 1.32)
Receptor status
Positive | 566 | 0.76 | (0.59, 0.98) | 0.69 | (0.48, 0.99)
Negative | 178 | 0.68 | (0.48, 0.97) | 0.66 | (0.44, 0.98)
* a hazard ratio of less than 1 indicates that TAC is associated with a longer disease free survival or overall survival compared to FAC.

14.3 Non-small Cell Lung Cancer (NSCLC)

The efficacy and safety of docetaxel has been evaluated in patients with unresectable, locally advanced or metastatic non-small cell lung cancer whose disease has failed prior platinum-based chemotherapy or in patients who are chemotherapy naive.

Monotherapy with docetaxel for NSCLC Previously Treated with Platinum-Based Chemotherapy

Two randomized, controlled trials established that a docetaxel dose of 75 mg/m^2 was tolerable and yielded a favorable outcome in patients previously treated with platinum-based chemotherapy (see below). Docetaxel at a dose of 100 mg/m^2, however, was associated with unacceptable hematologic toxicity, infections, and treatment-related mortality and this dose should not be used [see Boxed Warning, Dosage and Administration (2.7), Warnings and Precautions (5.3)].

One trial (TAX317), randomized patients with locally advanced or metastatic non-small cell lung cancer, a history of prior platinum-based chemotherapy, no history of taxane exposure, and an ECOG performance status ≤2 to docetaxel or best supportive care. The primary endpoint of the study was survival. Patients were initially randomized to docetaxel 100 mg/m^2 or best supportive care, but early toxic deaths at this dose led to a dose reduction to docetaxel 75 mg/m^2. A total of 104 patients were randomized in this amended study to either docetaxel 75 mg/m^2 or best supportive care.

In a second randomized trial (TAX320), 373 patients with locally advanced or metastatic nonsmall cell lung cancer, a history of prior platinum-based chemotherapy, and an ECOG performance status ≤2 were randomized to docetaxel 75 mg/m^2, docetaxel 100 mg/m^2 and a treatment in which the investigator chose either vinorelbine 30 mg/m^2 days 1, 8, and 15 repeated every 3 weeks or ifosfamide 2 g/m^2 days 1-3 repeated every 3 weeks. Forty percent of the patients in this study had a history of prior paclitaxel exposure. The primary endpoint was survival in both trials. The efficacy data for the docetaxel 75 mg/m^2 arm and the comparator arms are summarized in Table 16 and Figures 3 and 4 showing the survival curves for the two studies.

Table 16: Efficacy of Docetaxel in the Treatment of Non-small Cell Lung Cancer Patients Previously Treated with a Platinum-Based Chemotherapy Regimen (Intent-toTreat Analysis)
 | TAX317 |  | TAX320
 | Docetaxel 75 mg/m^2 n=55 | Best Supportive Care n=49 | Docetaxel 75 mg/m^2 n=125 | Control (V/I*) n=123
Overall Survival Log-rank Test | p=0.01 |  | p=0.13
Risk Ratio††, Mortality (Docetaxel: Control) | 0.56 |  | 0.82
95% CI (Risk Ratio) | (0.35, 0.88) |  | (0.63, 1.06)
Median Survival 95% CI | 7.5 months** (5.5, 12.8) | 4.6 months (3.7, 6.1) | 5.7 months (5.1, 7.1) | 5.6 months (4.4, 7.9)
% 1-year Survival 95% CI | 37%**† (24, 50) | 12% (2, 23) | 30%**† (22, 39) | 20% (13, 27)
Time to Progression 95% CI | 12.3 weeks** (9.0, 18.3) | 7.0 weeks (6.0, 9.3) | 8.3 weeks (7.0, 11.7) | 7.6 weeks (6.7, 10.1)
Response Rate 95% CI | 5.5% (1.1, 15.1) | Not Applicable | 5.7% (2.3, 11.3) | 0.8% (0.0, 4.5)
*Vinorelbine/Ifosfamide
**p≤0.05
†uncorrected for multiple comparisons
††a value less than 1.00 favors docetaxel

Only one of the two trials (TAX317) showed a clear effect on survival, the primary endpoint; that trial also showed an increased rate of survival to one year. In the second study (TAX320) the rate of survival at one year favored docetaxel 75 mg/m^2.

Figure 3: TAX317 Survival K-M Curves - Docetaxel 75 mg/m^2 Versus Best Supportive Care

Figure 4: TAX320 Survival K-M Curves - Docetaxel 75 mg/m^2 Versus Vinorelbine or Ifosfamide Control

Patients treated with docetaxel at a dose of 75 mg/m^2 experienced no deterioration in performance status and body weight relative to the comparator arms used in these trials.

Combination Therapy with docetaxel for Chemotherapy-Naive NSCLC

In a randomized controlled trial (TAX326), 1218 patients with unresectable stage IIIB or IV NSCLC and no prior chemotherapy were randomized to receive one of three treatments: docetaxel 75 mg/m^2 as a 1 hour infusion immediately followed by cisplatin 75 mg/m^2 over 30 to 60 minutes every 3 weeks; vinorelbine 25 mg/m^2 administered over 6-10 minutes on days 1, 8, 15, 22 followed by cisplatin 100 mg/m^2 administered on day 1 of cycles repeated every 4 weeks; or a combination of docetaxel and carboplatin.

The primary efficacy endpoint was overall survival. Treatment with docetaxel+cisplatin did not result in a statistically significantly superior survival compared to vinorelbine+cisplatin (see table below). The 95% confidence interval of the hazard ratio (adjusted for interim analysis and multiple comparisons) shows that the addition of docetaxel to cisplatin results in an outcome ranging from a 6% inferior to a 26% superior survival compared to the addition of vinorelbine to cisplatin. The results of a further statistical analysis showed that at least (the lower bound of the 95% confidence interval) 62% of the known survival effect of vinorelbine when added to cisplatin (about a 2-month increase in median survival; Wozniak et al. JCO, 1998) was maintained. The efficacy data for the docetaxel+cisplatin arm and the comparator arm are summarized in Table 17.

Table 17: Survival Analysis of Docetaxel in Combination Therapy for Chemotherapy- Naive NSCLC
Comparison | Docetaxel + Cisplatin n=408 | Vinorelbine + Cisplatin n=405
Kaplan-Meier Estimate of Median Survival | 10.9 months | 10.0 months
p-valuea | 0.122
Estimated Hazard Ratiob | 0.88
Adjusted 95% CIc | (0.74, 1.06)
aFrom the superiority test (stratified log rank) comparing docetaxel+cisplatin to vinorelbine+cisplatin
bHazard ratio of docetaxel+cisplatin versus vinorelbine+cisplatin. A hazard ratio of less than 1 indicates that
docetaxel+cisplatin is associated with a longer survival.
cAdjusted for interim analysis and multiple comparisons.

The second comparison in the same three-arm study, vinorelbine+cisplatin versus docetaxel+carboplatin, did not demonstrate superior survival associated with the docetaxel arm (Kaplan-Meier estimate of median survival was 9.1 months for docetaxel+carboplatin compared to 10.0 months on the vinorelbine+cisplatin arm) and the docetaxel+carboplatin arm did not demonstrate preservation of at least 50% of the survival effect of vinorelbine added to cisplatin. Secondary endpoints evaluated in the trial included objective response and time to progression. There was no statistically significant difference between docetaxel+cisplatin and vinorelbine+cisplatin with respect to objective response and time to progression (see Table 18).

Table 18: Response and TTP Analysis of Docetaxel in Combination Therapy for Chemotherapy-Naive NSCLC
Endpoint | Docetaxel + Cisplatin | Vinorelbine + Cisplatin | p-value
Objective Response Rate (95% CI)a | 31.6% (26.5%, 36.8%) | 24.4% (19.8%, 29.2%) | Not Significant
Median Time to Progressionb (95% CI)a | 21.4 weeks (19.3, 24.6) | 22.1 weeks (18.1, 25.6) | Not Significant
aAdjusted for multiple comparisons.
bKaplan-Meier estimates.

14.4 Castration-Resistant Prostate Cancer

The safety and efficacy of docetaxel in combination with prednisone in patients with metastatic castration-resistant prostate cancer were evaluated in a randomized multicenter active control trial. A total of 1006 patients with Karnofsky Performance Status (KPS) ≥60 were randomized to the following treatment groups:

- Docetaxel 75 mg/m^2every 3 weeks for 10 cycles.
- Docetaxel 30 mg/m^2administered weekly for the first 5 weeks in a 6-week cycle for 5 cycles.
- Mitoxantrone 12 mg/m^2every 3 weeks for 10 cycles.

All 3 regimens were administered in combination with prednisone 5 mg twice daily, continuously.

In the docetaxel every three week arm, a statistically significant overall survival advantage was demonstrated compared to mitoxantrone. In the docetaxel weekly arm, no overall survival advantage was demonstrated compared to the mitoxantrone control arm. Efficacy results for the docetaxel every 3 week arm versus the control arm are summarized in Table 19 and Figure 5.

Table 19: Efficacy of Docetaxel in the Treatment of Patients with Metastatic Castration Resistant Prostate Cancer (Intent-to-Treat Analysis)
 | Docetaxel + Prednisone every 3 weeks | Mitoxantrone + Prednisone every 3 weeks
Number of patients | 335 | 337
Median survival (months) | 18.9 | 16.5
95% CI | (17.0-21.2) | (14.4-18.6)
Hazard ratio | 0.761 | --
95% CI | (0.619-0.936) | --
p-value* | 0.0094 | --
*Stratified log-rank test. Threshold for statistical significance = 0.0175 because of 3 arms.

Figure 5: TAX327 Survival K-M Curves

14.5 Gastric Adenocarcinoma

A multicenter, open-label, randomized trial was conducted to evaluate the safety and efficacy of docetaxel for the treatment of patients with advanced gastric adenocarcinoma, including adenocarcinoma of the gastroesophageal junction, who had not received prior chemotherapy for advanced disease. A total of 445 patients with KPS >70 were treated with either docetaxel (T) (75 mg/m^2 on day 1) in combination with cisplatin (C) (75 mg/m^2 on day 1) and fluorouracil (F) (750 mg/m^2 per day for 5 days) or cisplatin (100 mg/m^2 on day 1) and fluorouracil (1000 mg/m^2 per day for 5 days). The length of a treatment cycle was 3 weeks for the TCF arm and 4 weeks for the CF arm. The demographic characteristics were balanced between the two treatment arms. The median age was 55 years, 71% were male, 71% were Caucasian, 24% were 65 years of age or older, 19% had a prior curative surgery and 12% had palliative surgery. The median number of cycles administered per patient was 6 (with a range of 1-16) for the TCF arm compared to 4 (with a range of 1-12) for the CF arm. Time to progression (TTP) was the primary endpoint and was defined as time from randomization to disease progression or death from any cause within 12 weeks of the last evaluable tumor assessment or within 12 weeks of the first infusion of study drugs for patients with no evaluable tumor assessment after randomization. The hazard ratio (HR) for TTP was 1.47 (CF/TCF, 95% CI: 1.19-1.83) with a significantly longer TTP (p=0.0004) in the TCF arm. Approximately 75% of patients had died at the time of this analysis. Overall survival was significantly longer (p=0.0201) in the TCF arm with a HR of 1.29 (95% CI: 1.04-1.61). Efficacy results are summarized in Table 20 and Figures 6 and 7.

Table 20: Efficacy of Docetaxel in the Treatment of Patients with Gastric Adenocarcinoma
Endpoint | TCF n=221 | CF n=224
Median TTP (months) | 5.6 | 3.7
(95% CI) | (4.86-5.91) | (3.45-4.47)
Hazard ratio† | 0.68
(95% CI) | (0.55-0.84)
*p-value | 0.0004
Median survival (months) | 9.2 | 8.6
(95% CI) | (8.38-10.58) | (7.16-9.46)
Hazard ratio† | 0.77
(95% CI) | (0.62-0.96)
*p-value | 0.0201
Overall Response Rate (CR+PR) (%) | 36.7 | 25.4
p-value | 0.0106
*Unstratified log-rank test

†For the hazard ratio (TCF/CF), values less than 1.00 favor the docetaxel arm.

Subgroup analyses were consistent with the overall results across age, gender and race.

Figure 6: Gastric Cancer Study (TAX325) Time to Progression K-M Curve

Figure 7: Gastric Cancer Study (TAX325) Survival K-M Curve

14.6 Head and Neck Cancer

Induction Chemotherapy Followed by Radiotherapy (TAX323)

The safety and efficacy of docetaxel in the induction treatment of patients with squamous cell carcinoma of the head and neck (SCCHN) was evaluated in a multicenter, open-label, randomized trial (TAX323). In this study, 358 patients with inoperable locally advanced SCCHN, and WHO performance status 0 or 1, were randomized to one of two treatment arms. Patients on the docetaxel arm received docetaxel (T) 75 mg/m^2 followed by cisplatin (P) 75 mg/m^2 on Day 1, followed by fluorouracil (F) 750 mg/m^2 per day as a continuous infusion on Days 1-5. The cycles were repeated every three weeks for 4 cycles. Patients whose disease did not progress received radiotherapy (RT) according to institutional guidelines (TPF/RT). Patients on the comparator arm received cisplatin (P) 100 mg/m^2 on Day 1, followed by fluorouracil (F) 1000 mg/m^2 /day as a continuous infusion on Days 1-5. The cycles were repeated every three weeks for 4 cycles. Patients whose disease did not progress received RT according to institutional guidelines (PF/RT). At the end of chemotherapy, with a minimal interval of 4 weeks and a maximal interval of 7 weeks, patients whose disease did not progress received radiotherapy (RT) according to institutional guidelines. Locoregional therapy with radiation was delivered either with a conventional fraction regimen (1.8 Gy-2.0 Gy once a day, 5 days per week for a total dose of 66 to 70 Gy) or with an accelerated/hyperfractionated regimen (twice a day, with a minimum interfraction interval of 6 hours, 5 days per week, for a total dose of 70 to 74 Gy, respectively). Surgical resection was allowed following chemotherapy, before or after radiotherapy.

The primary endpoint in this study, progression-free survival (PFS), was significantly longer in the TPF arm compared to the PF arm, p=0.0077 (median PFS: 11.4 vs 8.3 months, respectively) with an overall median follow-up time of 33.7 months. Median overall survival with a median follow-up of 51.2 months was also significantly longer in favor of the TPF arm compared to the PF arm (median OS: 18.6 vs 14.2 months, respectively). Efficacy results are presented in Table 21 and Figures 8 and 9.

Table 21: Efficacy of Docetaxel in the Induction Treatment of Patients with Inoperable Locally Advanced SCCHN (Intent-to-Treat Analysis)
Endpoint | Docetaxel + Cisplatin + Fluorouracil n=177 | Cisplatin + Fluorouracil n=181
Median progression free survival (months) | 11.4 | 8.3
(95% CI) | (10.1-14.0) | (7.4-9.1)
Adjusted Hazard ratio | 0.71
(95% CI) | (0.56-0.91)
*p-value | 0.0077
Median survival (months) | 18.6 | 14.2
(95% CI) | (15.7-24.0) | (11.5-18.7)
Hazard ratio | 0.71
(95% CI) | (0.56-0.90)
**p-value | 0.0055
Best overall response (CR + PR) to chemotherapy (%) | 67.8 | 53.6
(95% CI) | (60.4-74.6) | (46.0-61.0)
***p-value | 0.006
Best overall response (CR + PR) to study treatment [chemotherapy +/- radiotherapy] (%) | 72.3 | 58.6
(95% CI) | (65.1-78.8) | (51.0-65.8)
***p-value | 0.006
A Hazard ratio of less than 1 favors docetaxel+cisplatin+fluorouracil
*Stratified log-rank test based on primary tumor site
**Stratified log-rank test, not adjusted for multiple comparisons
***Chi square test, not adjusted for multiple comparisons

Figure 8: TAX323 Progression-Free Survival K-M Curve

Figure 9: TAX323 Overall Survival K-M Curve

Induction Chemotherapy Followed by Chemoradiotherapy (TAX324)

The safety and efficacy of docetaxel in the induction treatment of patients with locally advanced (unresectable, low surgical cure, or organ preservation) SCCHN was evaluated in a randomized, multicenter open-label trial (TAX324). In this study, 501 patients, with locally advanced SCCHN, and a WHO performance status of 0 or 1, were randomized to one of two treatment arms. Patients on the docetaxel arm received docetaxel (T) 75 mg/m^2 by intravenous infusion on day 1 followed by cisplatin (P) 100 mg/m^2 administered as a 30-minute to three-hour intravenous infusion, followed by the continuous intravenous infusion of fluorouracil (F) 1000 mg/m^2 /day from day 1 to day 4. The cycles were repeated every 3 weeks for 3 cycles. Patients on the comparator arm received cisplatin (P) 100 mg/m^2 as a 30-minute to three-hour intravenous infusion on day 1 followed by the continuous intravenous infusion of fluorouracil (F) 1000 mg/m^2 /day from day 1 to day 5. The cycles were repeated every 3 weeks for 3 cycles.

All patients in both treatment arms who did not have progressive disease were to receive 7 weeks of chemoradiotherapy (CRT) following induction chemotherapy 3 to 8 weeks after the start of the last cycle. During radiotherapy, carboplatin (AUC 1.5) was given weekly as a one-hour intravenous infusion for a maximum of 7 doses. Radiation was delivered with megavoltage equipment using once daily fractionation (2 Gy per day, 5 days per week for 7 weeks for a total dose of 70-72 Gy). Surgery on the primary site of disease and/or neck could be considered at any time following completion of CRT.

The primary efficacy endpoint, overall survival (OS), was significantly longer (log-rank test, p=0.0058) with the docetaxel-containing regimen compared to PF (median OS: 70.6 vs 30.1 months, respectively, hazard ratio [HR]=0.70, 95% confidence interval [CI]=0.54-0.90). Overall survival results are presented in Table 22 and Figure 10.

Table 22: Efficacy of Docetaxel in the Induction Treatment of Patients with Locally Advanced SCCHN (Intent-to-Treat Analysis)
Endpoint | Docetaxel + Cisplatin + Fluorouracil n=255 | Cisplatin + Fluorouracil n=246
Median overall survival (months) | 70.6 | 30.1
(95% CI) | (49.0-NE) | (20.9-51.5)
Hazard ratio: | 0.70
(95% CI) | (0.54-0.90)
*p-value | 0.0058
A Hazard ratio of less than 1 favors docetaxel+cisplatin+fluorouracil *unadjusted log-rank test
NE - not estimable

Figure 10: TAX324 Overall Survival K-M Curve

15 REFERENCES

1. "OSHA Hazardous Drugs." http://www.osha.gov/SLTC/hazardousdrugs/index.html

16 HOW SUPPLIED/STORAGE AND HANDLING

16.1 How Supplied

BEIZRAY injection is a clear, colorless liquid supplied as follows:

- Co-packaged kit containing BEIZRAY vial(s) and IV Solution Stabilizer (25% Albumin Human USP), a clear and slightly viscous solution
- Carton containing one BEIZRAY vial only

Package Configuration | BEIZRAY Strength | Carton Contents | NDC Number
80 mg kit | 80 mg/4 mL | one single-dose vial of 80 mg/4 mL BEIZRAY injection (NDC 70710-2090-1). one single-dose vial of 50 mL of 25% Albumin Human USP solution (NDC 64208-2512-4). | NDC 70710-2091-3
160 mg kit | 80 mg/4 mL | two single-dose vials of 80 mg/4 mL BEIZRAY injection (NDC 70710-2090-1). one single-dose vial of 50 mL of 25% Albumin Human USP solution (NDC 64208-2512-4). | NDC 70710-2093-4
20 mg/mL vial | 20 mg/mL | one single-dose vial of 20 mg/mL BEIZRAY injection. (NDC 70710-2092-1) | NDC 70710-2092-8
80 mg/4 mL vial | 80 mg/4 mL | One single-dose vial of 80 mg/4 mL BEIZRAY injection. (70710-2090-1) | NDC 70710-2152-1

16.2 Storage

BEIZRAY Injection and 25% Albumin Human USP (IV Solution Stabilizer):

Store at 20°C to 25°C (68°F to 77°F). Excursions permitted from 15°C to 30°C (59°F to 86°F). [see USP controlled room temperature]. Retain in the original package to protect from light. Protect from freezing.

16.3 Handling and Disposal

BEIZRAY is a hazardous drug. Follow applicable special handling and disposal procedures.

17 PATIENT COUNSELING INFORMATION

Advise the patient to read the FDA-approved patient labeling (Patient Information).

Bone Marrow Suppression

Advise patients that periodic assessment of their blood count will be performed to detect neutropenia, thrombocytopenia, and/ or anemia [see Contraindications (4), Warnings and Precautions (5.3)]. Instruct patients to monitor their temperature frequently and immediately report any occurrence of fever.

Enterocolitis and Neutropenic Colitis

Advise patients of the symptoms of colitis, such as abdominal pain or tenderness, and/or diarrhea, with or without fever, and instruct patients to promptly contact their healthcare provider if they experience these symptoms [see Dosage and Administration (2.7) and Warnings and Precautions (5.4)].

Hypersensitivity Reactions

Ask patients whether they have previously received paclitaxel therapy, and if they have experienced a hypersensitivity reaction to paclitaxel. Instruct patients to immediately report to their healthcare provider signs of a hypersensitivity reaction [see Contraindications (4), Warnings and Precautions (5.5)].

Fluid Retention

Advise patients to report signs of fluid retention such as peripheral edema in the lower extremities, weight gain, and dyspnea immediately to their healthcare provider [see Warnings and Precautions (5.6)].

Second Primary Malignancies

Advise patients on the risk of second primary malignancies during treatment with BEIZRAY [see Warnings and Precautions (5.7)].

Cutaneous Reactions

Advise patients that localized erythema of the extremities and severe skin toxicities may occur. Instruct patients to immediately report severe cutaneous reactions to their healthcare provider [see Dosage and Administration (2.7) and Warnings and Precautions (5.8)].

Neurologic Reactions

Advise patients that neurosensory symptoms or peripheral neuropathy may occur. Instruct patients to immediately report neurologic reactions to their healthcare provider [see Dosage and Administration (2.7) and Warnings and Precautions (5.9)].

Eye Disorders

Advise patients that vision disturbances and excessive tearing are associated with BEIZRAY administration. Instruct patients to immediately report any vision changes to their healthcare provider [see Warnings and Precautions (5.10)].

Gastrointestinal Reactions

Explain to patients that nausea, vomiting, diarrhea, and constipation are associated with BEIZRAY administration. Instruct patients to report any severe events to their healthcare provider [see Adverse Reactions (6)].

Cardiac Disorders

Advise patients to report any irregular and/or rapid heartbeat, severe shortness of breath, dizziness, and/or fainting immediately to their healthcare provider [see Adverse Reactions (6)].

Other Common Adverse Reactions

Advise patients that other common adverse reactions associated with BEIZRAY may include alopecia (cases of permanent hair loss have been reported), asthenia, anorexia, dysgeusia, mucositis, myalgia, nail disorders, or pain. Instruct patients to report these reactions to their healthcare provider if serious events occur [see Adverse Reactions (6)].

Importance of Corticosteroids

Explain the significance of oral corticosteroids such as dexamethasone administration to the patient to help facilitate compliance. Instruct patients to report to their healthcare provider if they were not compliant with the oral corticosteroid regimen [see Dosage and Administration (2.6)].

Embryo-Fetal Toxicity

BEIZRAY can cause fetal harm. Advise patients to inform their healthcare provider of a known or suspected pregnancy. Advise patients to avoid becoming pregnant while receiving this drug. Advise female patients of reproductive potential to use effective contraceptives during treatment and for 2 months after the last dose of BEIZRAY. Advise male patients with female partners of reproductive potential to use effective contraception during treatment and for 4 months after the last dose of BEIZRAY [see Warnings and Precautions (5.12), and Use in Specific Populations (8.1, 8.3)].

Lactation

Advise women not to breastfeed during BEIZRAY treatment and for 1 week after the last dose [see Use in Specific Populations (8.2)].

Infertility

Advise males of reproductive potential that BEIZRAY may impair fertility [see Nonclinical Toxicology (13.1)].

Alcohol Content in BEIZRAY

Explain to patients the possible effects of the alcohol content in BEIZRAY, including possible effects on the central nervous system [see Warnings and Precautions (5.13)].

Tumor Lysis Syndrome

Advise patients of the potential risk of tumor lysis syndrome and to immediately report any signs or symptoms associated with this event (nausea, vomiting, confusion, shortness of breath, seizure, irregular heartbeat, dark or cloudy urine, reduced amount of urine, unusual tiredness, muscle cramps) to their healthcare provider. Advise patients of the importance of keeping scheduled appointment for blood work or other laboratory tests and of drinking adequate fluids to avoid dehydration. [see Warnings and Precautions (5.14)].

Ability to Drive or Operate Machines

Explain to patients that BEIZRAY may impair their ability to drive or operate machines due to its side effects [see Adverse Reactions (6)] or due to the alcohol content of BEIZRAY [see Warnings and Precautions (5.13)]. Advise them not to drive or use machines if they experience these side effects during treatment.

Drug Interactions

Inform patients about the risk of drug interactions and the importance of providing a list of prescription and non-prescription drugs to their healthcare provider [see Drug Interactions (7)].

Manufactured by:

Made in China

Distributed by:

Zydus Pharmaceuticals (USA) Inc.

Pennington, NJ 08534

PATIENT INFORMATION
BEIZRAY (BAY-zer-ray)
(docetaxel) injection
for intravenous use

What is the most important information I should know about BEIZRAY?
BEIZRAY can cause serious side effects, including death.

- The chance of death in people who receive BEIZRAY is higher if you:

o have liver problems
o receive high doses of BEIZRAY
o have non-small cell lung cancer and have been treated with chemotherapy medicines that contain platinum

- BEIZRAY can affect your blood cells. Your healthcare provider should do routine blood tests during treatment with BEIZRAY. This will include regular checks of your white blood cell counts. If your white blood cells are too low, your healthcare provider may not treat you with BEIZRAY until you have enough white blood cells. People with low white blood cell counts can develop life-threatening infections. The earliest sign of infection may be fever. Follow your healthcare provider's instructions for how often to take your temperature during treatment with BEIZRAY. Call your healthcare provider right away if you have a fever.
- Swelling (inflammation) of the small intestine and colon. This can happen at any time during treatment and could lead to death as early as the first day you get symptoms. Tell your healthcare provider right away if you develop new or worse symptoms of intestinal problems, including stomach (abdominal) pain or tenderness or diarrhea, with or without fever.
- Severe allergic reactions are medical emergencies that can happen in people who receive BEIZRAY and can lead to death. You may be at higher risk of developing a severe allergic reaction to BEIZRAY if you are allergic to paclitaxel. Your healthcare provider will monitor you closely for allergic reactions during your BEIZRAY infusion.

Tell your healthcare provider right away if you have any of these signs of a severe allergic reaction:
o trouble breathing
o sudden swelling of your face, lips, tongue, throat, or trouble swallowing

- hives (raised bumps), rash, or redness all over your body

- Your body may hold too much fluid (severe fluid retention) during treatment with BEIZRAY. This can be life threatening. To decrease the chance of this happening, you must take another medicine, a corticosteroid, before each BEIZRAY treatment. You may take the corticosteroid exactly as your healthcare provider tells you. Tell your healthcare provider or nurse before your BEIZRAY treatment if you forgot to take your corticosteroid dose or do not take it as your healthcare provider tells you. Tell your healthcare provider right away if you have swelling in your legs or feet, weight gain or shortness of breath.
- Risk of new cancers. An increase in new (second) cancers has happened in people treated with BEIZRAY together with certain other anticancer treatments. This includes certain blood cancers, such as acute myeloid leukemia (AML), myelodysplastic syndrome (MDS), non-Hodgkin's Lymphoma (NHL), and kidney cancer.

o Changes in blood counts due to leukemia and other blood disorders may occur years after treatment with BEIZRAY.
Your healthcare provider will check you for new cancers during and after your treatment with BEIZRAY.

- Severe skin problems.

Tell your healthcare provider right away if you have any of these signs of a severe skin reaction:

- redness and swelling of your arms and legs.
- blistering, peeling, or bleeding on any part of your skin (including your lips, eyes, mouth, nose, genitals, hands or feet) with or without a rash. You may also have flu-like symptoms such as fever, chills, or muscle aches.
- red, scaly rash all over your body with blisters, small red or white bumps under the skin that contain pus (pustules), and fever.

What is BEIZRAY?
BEIZRAY is a prescription anticancer medicine used to treat certain people with:

- breast cancer
- non-small cell lung cancer
- prostate cancer
- stomach cancer
- head and neck cancer

It is not known if BEIZRAY is effective in children.

Do not receive BEIZRAY if you:

- have a low white blood cell count.
- have had a severe allergic reaction to:

- docetaxel, the active ingredient in BEIZRAY

See "What is the most important information I should know about BEIZRAY?" for the signs and symptoms of a severe allergic reaction.
See the end of this Patient Information for a complete list of the ingredients in BEIZRAY.

Before you receive BEIZRAY, tell your healthcare provider about all of your medical conditions, including if you:

- are allergic to any medicines, including paclitaxel. See "Do not receive BEIZRAY if you" .
- have liver problems
- have kidney problems
- are pregnant or plan to become pregnant. BEIZRAY can harm your unborn baby. You should not become pregnant during treatment with BEIZRAY. Tell your healthcare provider if you become pregnant or you think you may be pregnant during treatment with BEIZRAY.

Females who are able to become pregnant:

- Your healthcare provider will check to see if you are pregnant before you start treatment with BEIZRAY.
- You should use effective birth control (contraception) during treatment with BEIZRAY and for 2 months after the last dose.

Males with female partners who are able to become pregnant should use effective birth control during treatment with BEIZRAY and for 4 months after the last dose.
Talk to your healthcare provider if you have questions about birth control options that are right for you.

- are breastfeeding or plan to breastfeed. It is not known if BEIZRAY passes into your breast milk. Do not breastfeed during treatment with BEIZRAY and for 1 week after the last dose.

Tell your healthcare provider about all the medicines you take, including prescription and over-the- counter medicines, vitamins, and herbal supplements. BEIZRAY may affect the way other medicines work, and other medicines may affect the way BEIZRAY works.
Know the medicines you take. Keep a list of them to show your healthcare provider and pharmacist when you get a new medicine.

How will I receive BEIZRAY?

- BEIZRAY will be given to you as an intravenous (IV) injection into your vein, usually over 1 hour.
- BEIZRAY is usually given every 3 weeks.
- Your healthcare provider will decide how long you will receive treatment with BEIZRAY.
- Your healthcare provider will check your blood cell counts and other blood tests during your treatment with BEIZRAY to check for side effects of BEIZRAY.
- Your healthcare provider may stop your treatment, change the timing of your treatment, or change the dose of your treatment if you have certain side effects while receiving BEIZRAY.

What are the possible side effects of BEIZRAY?
BEIZRAY may cause serious side effects including death.

- See "What is the most important information I should know about BEIZRAY?"
- Neurologic problems. Neurologic symptoms are common in people who receive BEIZRAY but can be severe. Tell your healthcare provider right away if you have numbness, tingling, or burning in your hands or feet (peripheral neuropathy) or weakness of your legs, feet, arms, or hands (motor weakness).
- Vision problems including blurred vision or loss of vision. Tell your healthcare provider right away if you have any vision changes.
- BEIZRAY injection contains alcohol. The alcohol content in BEIZRAY may impair your ability to drive or use machinery right after receiving BEIZRAY. Consider whether you should drive, operate machinery or do other dangerous activities right after you receive BEIZRAY treatment.
- Tumor lysis syndrome (TLS). TLS is caused by the fast breakdown of cancer cells. TLS can cause kidney failure, the need for dialysis treatment, or heart problems, and may lead to death.

Your healthcare provider will do blood tests to check for TLS when you first start treatment and during treatment with BEIZRAY. Tell your healthcare provider right away if you have any symptoms of TLS during treatment with BEIZRAY, including:

- nausea

- irregular heartbeat

- vomiting

- dark or cloudy urine

- confusion

- reduced amount of urine

- shortness of breath

- unusual tiredness

- muscle cramps

You may experience side effects of this medicine that may impair your ability to drive, use tools, or operate machines. If this happens, do not drive or use any tools or machines before discussing with your healthcare provider.

The most common side effects of BEIZRAY include:

- infections

- feeling weak or tired

- low white blood cells (help fight infections), low red blood cells (anemia) and low platelets (help blood to clot)

- joint and muscle pain

- allergic reactions (See "What is the most important information I should know about BEIZRAY?")

- nausea and vomiting

- changes in your sense of taste

- diarrhea

- shortness of breath

- mouth or lip sores

- constipation

- hair loss: in some people, permanent hair loss has been reported

- decreased appetite

- redness of the eye, excess tearing

- changes in your fingernails or toenails

- skin reactions at the site of BEIZRAY administration such as increased skin pigmentation, redness, tenderness, swelling, warmth or dryness of the skin

- swelling of your hands, face or feet

- tissue damage if BEIZRAY leaks out of the vein into the tissues

Tell your healthcare provider if you have a fast or irregular heartbeat, severe shortness of breath, dizziness or fainting during your infusion. If any of these events occurs after your infusion, get medical help right way.
BEIZRAY may affect fertility in males. Talk to your healthcare provider if this is a concern for you.
These are not all of the possible side effects of BEIZRAY. For more information, ask your healthcare provider or pharmacist.
Call your healthcare provider for medical advice about side effects. You may report side effects to FDA at 1-800-FDA-1088.

General information about the safe and effective use of BEIZRAY.
Medicines are sometimes prescribed for purposes other than those listed in this Patient Information. You can ask your pharmacist or healthcare provider for information about BEIZRAY that is written for health professionals.

What are the ingredients in BEIZRAY?
Active ingredient: docetaxel
Inactive ingredients: dehydrated alcohol solution, with citric acid for pH adjustment.
25% Albumin Human USP contains sodium acetyltryptophanate and sodium caprylate.
Manufactured by:
Made in China
Distributed by:
Zydus Pharmaceuticals (USA) Inc.
Pennington, NJ 08534
For more information, call 1-877-993-8779.

This Patient Information has been approved by the U.S. Food and Drug Administration Issued: 12/2025

Every three-week injection of BEIZRAY for breast, non-small cell lung and stomach, and head and neck cancers
Take your oral corticosteroid medicine as your healthcare provider tells you.
Oral corticosteroid dosing:
Day 1 Date: Time: ___ AM ___ PM
Day 2 Date: Time: ___ AM ___ PM
(BEIZRAY Treatment Day)
Day 3 Date: Time: ___ AM ___ PM

Every three-week injection of BEIZRAY for prostate cancer
Take your oral corticosteroid medicine as your
healthcare provider tells you.
Oral corticosteroid dosing:
Date: Time: ______
Date: Time: ______
(BEIZRAY Treatment Day)
Time: _____

PACKAGE LABEL.PRINCIPAL DISPLAY PANEL

BEIZRAY (docetaxel) Injection

80 mg/4 mL (20 mg/mL)

For Intravenous Infusion Only

Must be diluted before use in a prepared Albumin (Human) in 0.9% Sodium Chloride Injection solution

Do not substitute BEIZRAY for other docetaxel products

Discard unused portion

Warning: Hazardous Drug

BEIZRAY (docetaxel) Injection, 80 mg/4 mL -Vial Label

BEIZRAY (docetaxel) Injection, 80 mg Kit -Carton Label

Each kit Contains:

-One 4 mL Single-dose vials of Beizray (docetaxel) Injection

-One 50 mL Single-dose vial of IV Solution Stabilizer (Human Albumin 25%)

BEIZRAY (docetaxel) Injection, 160 mg Kit -Carton Label

Each kit Contains:

-Two 4 mL Single-dose vials of Beizray (docetaxel) Injection

-One 50 mL Single-dose vial of IV Solution Stabilizer (Human Albumin 25%)

BEIZRAY (docetaxel) Injection, 80 mg single-dose vial -Carton Label

Contains One 4 mL Single-dose vial of Beizray (docetaxel) Injection only

BEIZRAY (docetaxel) Injection

20 mg/mL

For Intravenous Infusion Only

Must be diluted before use in a prepared Albumin (Human) in 0.9% Sodium Chloride Injection solution

Do not substitute BEIZRAY for other docetaxel products

Discard unused portion

Warning: Hazardous Drug

BEIZRAY (docetaxel) Injection, 20 mg/mL -Vial Label

BEIZRAY (docetaxel) Injection, 20 mg single-dose vial -Carton Label

Contains One 1 mL Single-dose vial of Beizray (docetaxel) Injection only